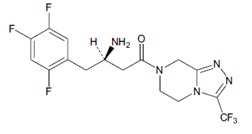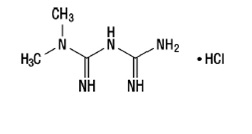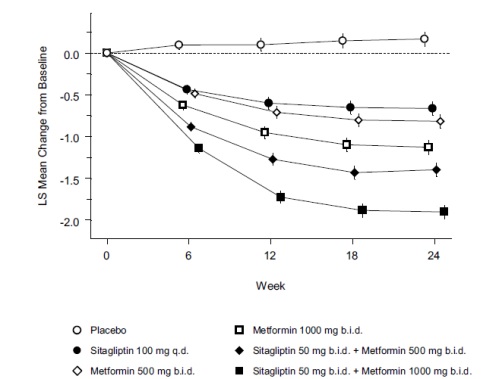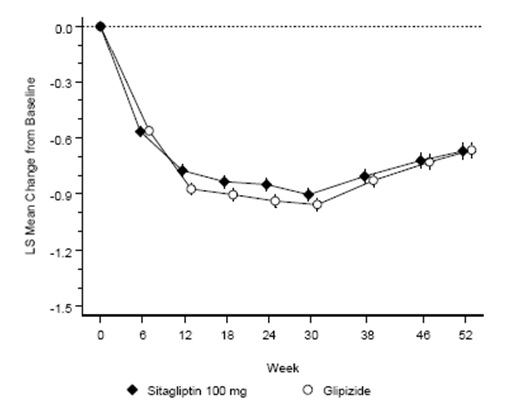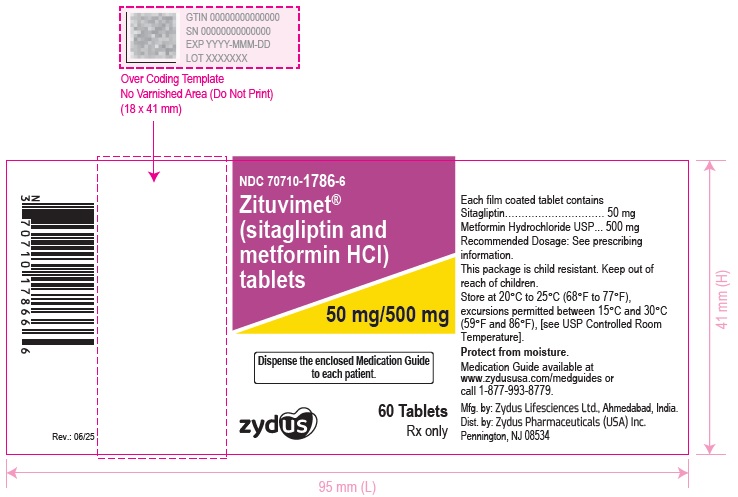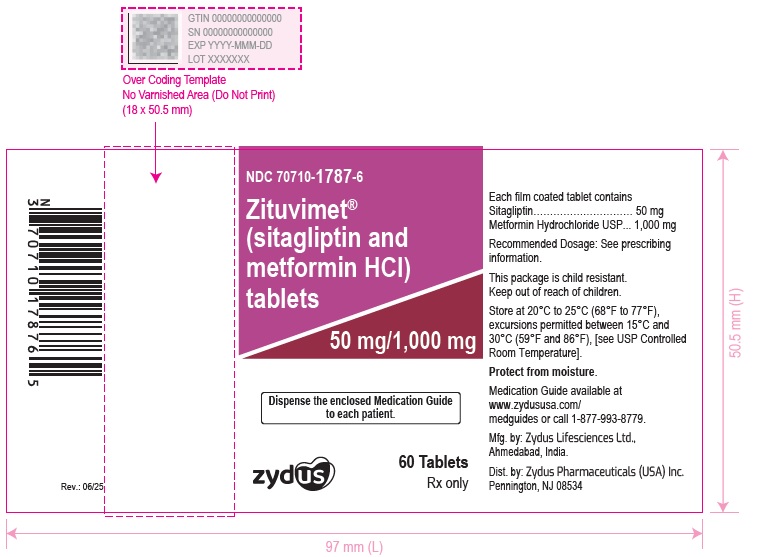 DRUG LABEL: ZITUVIMET
NDC: 70710-1786 | Form: TABLET, FILM COATED
Manufacturer: Zydus Pharmaceuticals (USA) Inc.
Category: prescription | Type: HUMAN PRESCRIPTION DRUG LABEL
Date: 20250609

ACTIVE INGREDIENTS: SITAGLIPTIN 50 mg/1 1; METFORMIN HYDROCHLORIDE 500 mg/1 1
INACTIVE INGREDIENTS: CROSCARMELLOSE SODIUM; LOW-SUBSTITUTED HYDROXYPROPYL CELLULOSE (11% HYDROXYPROPYL; 120000 MW); MAGNESIUM STEARATE; MALIC ACID; MICROCRYSTALLINE CELLULOSE; POLYETHYLENE GLYCOL 3350; POLYVINYL ALCOHOL, UNSPECIFIED; POVIDONE K30; SILICON DIOXIDE; SODIUM STEARYL FUMARATE; TALC; TITANIUM DIOXIDE

HIGHLIGHTS OF PRESCRIBING INFORMATION

These highlights do not include all the information needed to use ZITUVIMET safely and effectively. See full prescribing information for ZITUVIMET.
ZITUVIMET® (sitagliptin and metformin hydrochloride) tablets, for oral use
Initial U.S. Approval: 2007

WARNING: LACTIC ACIDOSIS

See full prescribing information for complete boxed warning.

- Postmarketing cases of metformin-associated lactic acidosis have resulted in death, hypothermia, hypotension, and resistant bradyarrhythmias. Symptoms included malaise, myalgias, respiratory distress, somnolence, and abdominal pain. Laboratory abnormalities included elevated blood lactate levels, anion gap acidosis, increased lactate/pyruvate ratio, and metformin plasma levels generally >5 mcg/mL. (5.1)
- Risk factors include renal impairment, concomitant use of certain drugs, age ≥65 years old, radiological studies with contrast, surgery and other procedures, hypoxic states, excessive alcohol intake, and hepatic impairment. Steps to reduce the risk of and manage metformin-associated lactic acidosis in these high-risk groups are provided in the Full Prescribing Information. (5.1)
- If lactic acidosis is suspected, discontinue ZITUVIMET and institute general supportive measures in a hospital setting. Prompt hemodialysis is recommended. (5.1)

1 INDICATIONS AND USAGE

ZITUVIMET is a combination of sitagliptin, a dipeptidyl peptidase-4 (DPP-4) inhibitor, and metformin hydrochloride (HCl), a biguanide, indicated as an adjunct to diet and exercise to improve glycemic control in adults with type 2 diabetes mellitus. (1)

Limitations of Use:

- ZITUVIMET is not recommended in patients with type 1 diabetes mellitus. (1)
- ZITUVIMET has not been studied in patients with a history of pancreatitis. (1)

2 DOSAGE AND ADMINISTRATION

- Take ZITUVIMET orally twice daily with meals. (2.1)
- Individualize the dosage of ZITUVIMET on the basis of the patient's current regimen, effectiveness, and tolerability. (2.1)
- The maximum recommended daily dose is 100 mg of sitagliptin and 2,000 mg of metformin HCl. (2.1)
- The recommended starting dose in patients not currently treated with metformin is 50 mg sitagliptin and 500 mg metformin HCl twice daily, with gradual dose escalation recommended to reduce gastrointestinal side effects associated with metformin. (2.1)
- The starting dose in patients already treated with metformin should provide sitagliptin dosed as 50 mg twice daily (100 mg total daily dose) and the dose of metformin already being taken. For patients taking metformin HCl 850 mg twice daily, the recommended starting dose of ZITUVIMET is 50 mg sitagliptin and 1,000 mg metformin HCl twice daily. (2.1)
- Prior to initiation, assess renal function with estimated glomerular filtration rate (eGFR) (2.2)

○ Do not use in patients with eGFR below 30 mL/min/1.73 m^2

○ ZITUVIMET is not recommended in patients with eGFR between 30 and less than 45 mL/min/1.73 m^2.

- ZITUVIMET may need to be discontinued at time of, or prior to, iodinated contrast imaging procedures. (2.3)

3 DOSAGE FORMS AND STRENGTHS

ZITUVIMET Tablets:

• sitagliptin 50 mg and metformin HCl 500 mg tablets

• sitagliptin 50 mg and metformin HCl 1,000 mg tablets (3)

4 CONTRAINDICATIONS

- Severe renal impairment: (eGFR below 30 mL/min/1.73 m^2) (4)
- Metabolic acidosis, including diabetic ketoacidosis. (4)
- History of a serious hypersensitivity reaction to ZITUVIMET, sitagliptin, or metformin, such as anaphylaxis or angioedema. (4)

5 WARNINGS AND PRECAUTIONS

- Lactic Acidosis: See boxed warning. (5.1)
- Pancreatitis: There have been postmarketing reports of acute pancreatitis, including fatal and non-fatal hemorrhagic or necrotizing pancreatitis. If pancreatitis is suspected, promptly discontinue ZITUVIMET. (5.2)
- Heart Failure: Has been observed with two other members of the DPP-4 inhibitor class. Consider risks and benefits of ZITUVIMET in patients who have known risk factors for heart failure. Monitor patients for signs and symptoms. (5.3)
- Acute Renal Failure: Has been reported postmarketing, sometimes requiring dialysis. Before initiating ZITUVIMET and at least annually thereafter, assess renal function. (5.4)
- Vitamin B12Deficiency: Metformin may lower vitamin B12levels. Measure hematologic parameters annually and vitamin B12at 2 to 3 year intervals and manage any abnormalities. (5.5)
- Hypoglycemia with Concomitant Use with Insulin or Insulin Secretagogues: Increased risk of hypoglycemia when used in combination with insulin and/or an insulin secretagogue. A lower dose of insulin or insulin secretagogue may be required. (5.6)
- Hypersensitivity Reactions: There have been postmarketing reports of serious allergic and hypersensitivity reactions in patients treated with sitagliptin such as anaphylaxis, angioedema, and exfoliative skin conditions including Stevens-Johnson syndrome. Promptly stop ZITUVIMET, assess for other potential causes, institute appropriate monitoring and treatment. (5.7)
- Severe and Disabling Arthralgia: Has been reported in patients taking DPP-4 inhibitors. Consider as a possible cause for severe joint pain and discontinue drug if appropriate. (5.8)
- Bullous Pemphigoid: There have been postmarketing reports requiring hospitalization in patients taking DPP-4 inhibitors. Tell patients to report development of blisters or erosions. If bullous pemphigoid is suspected, discontinue ZITUVIMET. (5.9)

6 ADVERSE REACTIONS

- Most common adverse reactions (incidence ≥5% of patients simultaneously started on sitagliptin and metformin and more commonly than in patients treated with placebo were diarrhea, upper respiratory tract infection, and headache. (6.1)

To report SUSPECTED ADVERSE REACTIONS, contact Zydus Pharmaceuticals (USA) Inc. at 1-877-993-8779 or FDA at 1-800-FDA-1088 or www.fda.gov/medwatch.

7 DRUG INTERACTIONS

- Carbonic anhydrase inhibitors may increase risk of lactic acidosis. Consider more frequent monitoring. (7)
- Drugs that reduce metformin clearance (such as ranolazine, vandetanib, dolutegravir, and cimetidine) may increase the accumulation of metformin. Consider the benefits and risks of concomitant use. (7)
- Alcohol can potentiate the effect of metformin on lactate metabolism. Warn patients against excessive alcohol intake. (7)

8 USE IN SPECIFIC POPULATIONS

- Females and Males of Reproductive Potential: Advise premenopausal females of the potential for an unintended pregnancy. (8.3)
- Geriatric Use: Assess renal function more frequently. (8.5)
- Hepatic Impairment: Avoid use in patients with hepatic impairment. (8.7)

FULL PRESCRIBING INFORMATION

WARNING: LACTIC ACIDOSIS

Postmarketing cases of metformin-associated lactic acidosis have resulted in death, hypothermia, hypotension, and resistant bradyarrhythmias. The onset of metformin-associated lactic acidosis is often subtle, accompanied only by nonspecific symptoms such as malaise, myalgias, respiratory distress, somnolence, and abdominal pain. Metformin-associated lactic acidosis was characterized by elevated blood lactate levels (>5 mmol/Liter), anion gap acidosis (without evidence of ketonuria or ketonemia), an increased lactate/pyruvate ratio, and metformin plasma levels generally >5 mcg/mL [see Warnings and Precautions (5.1)].

Risk factors for metformin-associated lactic acidosis include renal impairment, concomitant use of certain drugs (e.g., carbonic anhydrase inhibitors such as topiramate), age 65 years old or greater, having a radiological study with contrast, surgery and other procedures, hypoxic states (e.g., acute congestive heart failure), excessive alcohol intake, and hepatic impairment.

Steps to reduce the risk of and manage metformin-associated lactic acidosis in these high risk groups are provided in the full prescribing information [see Dosage and Administration (2.2)>, Contraindications (4), Warnings and Precautions (5.1), Drug Interactions (7), and Use in Specific Populations (8.6, 8.7)].

If metformin-associated lactic acidosis is suspected, immediately discontinue ZITUVIMET and institute general supportive measures in a hospital setting. Prompt hemodialysis is recommended [see Warnings and Precautions (5.1)].

1 INDICATIONS AND USAGE

ZITUVIMET is indicated as an adjunct to diet and exercise to improve glycemic control in adults with type 2 diabetes mellitus.

Limitations of Use

ZITUVIMET is not recommended in patients with type 1 diabetes mellitus.

ZITUVIMET has not been studied in patients with a history of pancreatitis. It is unknown whether patients with a history of pancreatitis are at increased risk for the development of pancreatitis while using ZITUVIMET. [see Warnings and Precautions (5.2)].

2 DOSAGE AND ADMINISTRATION

2.1 Recommended Dosage

- Take ZITUVIMET orally twice daily with meals.
- Individualize the dosage of ZITUVIMET on the basis of the patient's current regimen, effectiveness, and tolerability.
- The maximum recommended daily dose is 100 mg of sitagliptin and 2,000 mg of metformin hydrochloride (HCl).
- Do not split or divide ZITUVIMET tablets.
- The recommended starting dose in patients not currently treated with metformin is 50 mg sitagliptin and 500 mg metformin HCl twice daily, with gradual dose escalation recommended to reduce gastrointestinal side effects associated with metformin.
- The starting dose in patients already treated with metformin should provide sitagliptin dosed as 50 mg twice daily (100 mg total daily dose) and the dose of metformin already being taken. For patients taking metformin HCl 850 mg twice daily, the recommended starting dose of ZITUVIMET is 50 mg sitagliptin and 1,000 mg metformin HCl twice daily.

2.2 Recommendations for Use in Renal Impairment

- Assess renal function prior to initiation of ZITUVIMET and periodically thereafter.
- ZITUVIMET is contraindicated in patients with an estimated glomerular filtration rate (eGFR) below 30 mL/min/1.73 m^2 [see Contraindications (4) and Warnings and Precautions (5.1)].
- ZITUVIMET is not recommended in patients with an eGFR between 30 and less than 45 mL/min/1.73 m^2because these patients require a lower dosage of sitagliptin than what is available in the fixed combination ZITUVIMET product.

2.3 Discontinuation for Iodinated Contrast Imaging Procedures

Discontinue ZITUVIMET at the time of, or prior to, an iodinated contrast imaging procedure in patients with an eGFR between 30 and 60 mL/min/1.73 m^2; in patients with a history of liver disease, alcoholism, or heart failure; or in patients who will be administered intra-arterial iodinated contrast. Re-evaluate eGFR 48 hours after the imaging procedure; restart ZITUVIMET if renal function is stable [see Warnings and Precautions (5.1)].

3 DOSAGE FORMS AND STRENGTHS

Tablets:

- sitagliptin 50 mg and metformin HCl 500 mg tablets are white to off-white, oval shaped, biconvex, film coated tablets debossed with "1786" on one side and plain on the other side.
- sitagliptin 50 mg and metformin HCl 1,000 mg tablets are reddish brown, oval shaped, biconvex, film coated tablets debossed with "1787" on one side and plain on the other side.

4 CONTRAINDICATIONS

ZITUVIMET is contraindicated in patients with:

- Severe renal impairment (eGFR below 30 mL/min/1.73 m^2) [see Warnings and Precautions (5.1)].
- Acute or chronic metabolic acidosis, including diabetic ketoacidosis.
- History of a serious hypersensitivity reaction to sitagliptin, metformin, or any of the excipients in ZITUVIMET. Serious hypersensitivity reactions including anaphylaxis or angioedema have been reported. [see Warnings and Precautions (5.7) and Adverse Reactions (6.2)].

5 WARNINGS AND PRECAUTIONS

5.1 Lactic Acidosis

There have been postmarketing cases of metformin-associated lactic acidosis, including fatal cases. These cases had a subtle onset and were accompanied by nonspecific symptoms such as malaise, myalgias, abdominal pain, respiratory distress, or increased somnolence; however, hypothermia, hypotension and resistant bradyarrhythmias have occurred with severe acidosis. Metformin-associated lactic acidosis was characterized by elevated blood lactate concentrations (>5 mmol/Liter), anion gap acidosis (without evidence of ketonuria or ketonemia), and an increased lactate/pyruvate ratio; metformin plasma levels were generally >5 mcg/mL. Metformin decreases liver uptake of lactate increasing lactate blood levels which may increase the risk of lactic acidosis, especially in patients at risk.

If metformin-associated lactic acidosis is suspected, general supportive measures should be instituted promptly in a hospital setting, along with immediate discontinuation of ZITUVIMET. In ZITUVIMET treated patients with a diagnosis or strong suspicion of lactic acidosis, prompt hemodialysis is recommended to correct the acidosis and remove accumulated metformin (metformin HCl is dialyzable, with a clearance of up to 170 mL/min under good hemodynamic conditions). Hemodialysis has often resulted in reversal of symptoms and recovery.

Educate patients and their families about the symptoms of lactic acidosis and if these symptoms occur instruct them to discontinue ZITUVIMET and report these symptoms to their health care provider.

For each of the known and possible risk factors for metformin-associated lactic acidosis, recommendations to reduce the risk of and manage metformin-associated lactic acidosis are provided below:

Renal Impairment

The postmarketing metformin-associated lactic acidosis cases primarily occurred in patients with significant renal impairment. The risk of metformin accumulation and metformin-associated lactic acidosis increases with the severity of renal impairment because metformin is substantially excreted by the kidney. Clinical recommendations based upon the patient's renal function include [see Dosage and Administration (2.2) and Clinical Pharmacology (12.3)]:

- Before initiating ZITUVIMET, obtain an estimated glomerular filtration rate (eGFR).
- ZITUVIMET is contraindicated in patients with an eGFR below 30 mL/min/1.73 m^2 [see Contraindications (4)].
- ZITUVIMET is not recommended in patients with an eGFR between 30 and less than 45 mL/min/1.73 m^2because these patients require a lower dosage of sitagliptin than what is available in the fixed combination ZITUVIMET product.
- Obtain an eGFR at least annually in all patients taking ZITUVIMET. In patients at increased risk for the development of renal impairment (e.g., the elderly), renal function should be assessed more frequently.

Drug Interactions

The concomitant use of ZITUVIMET with specific drugs may increase the risk of metformin-associated lactic acidosis: those that impair renal function, result in significant hemodynamic change, interfere with acid-base balance or increase metformin accumulation [see Drug Interactions (7)]. Therefore, consider more frequent monitoring of patients.

Age 65 or Greater

The risk of metformin-associated lactic acidosis increases with the patient's age because elderly patients have a greater likelihood of having hepatic, renal, or cardiac impairment than younger patients. Assess renal function more frequently in elderly patients [see Use in Specific Populations (8.5)].

Radiological Studies with Contrast

Administration of intravascular iodinated contrast agents in metformin-treated patients has led to an acute decrease in renal function and the occurrence of lactic acidosis. Stop ZITUVIMET at the time of, or prior to, an iodinated contrast imaging procedure in patients with an eGFR between 30 and 60 mL/min/1.73 m^2; in patients with a history of hepatic impairment, alcoholism, or heart failure; or in patients who will be administered intra-arterial iodinated contrast. Re-evaluate eGFR 48 hours after the imaging procedure, and restart ZITUVIMET if renal function is stable.

Surgery and Other Procedures

Withholding of food and fluids during surgical or other procedures may increase the risk for volume depletion, hypotension and renal impairment. ZITUVIMET should be temporarily discontinued while patients have restricted food and fluid intake.

Hypoxic States

Several of the postmarketing cases of metformin-associated lactic acidosis occurred in the setting of acute congestive heart failure (particularly when accompanied by hypoperfusion and hypoxemia). Cardiovascular collapse (shock), acute myocardial infarction, sepsis, and other conditions associated with hypoxemia have been associated with lactic acidosis and may also cause prerenal azotemia. When such events occur, discontinue ZITUVIMET.

Excessive Alcohol Intake

Alcohol potentiates the effect of metformin on lactate metabolism and this may increase the risk of metformin-associated lactic acidosis. Warn patients against excessive alcohol intake while receiving ZITUVIMET.

Hepatic Impairment

Patients with hepatic impairment have developed with cases of metformin-associated lactic acidosis. This may be due to impaired lactate clearance resulting in higher lactate blood levels. Therefore, avoid use of ZITUVIMET in patients with clinical or laboratory evidence of hepatic disease.

5.2 Pancreatitis

There have been postmarketing reports of acute pancreatitis, including fatal and non-fatal hemorrhagic or necrotizing pancreatitis, in patients taking ZITUVIMET. After initiation of ZITUVIMET, patients should be observed carefully for signs and symptoms of pancreatitis. If pancreatitis is suspected, sitagliptin should promptly be discontinued and appropriate management should be initiated. It is unknown whether patients with a history of pancreatitis are at increased risk for the development of pancreatitis while using ZITUVIMET.

5.3 Heart Failure

An association between DPP-4 inhibitor treatment and heart failure has been observed in cardiovascular outcomes trials for two other members of the DPP-4 inhibitor class. These trials evaluated patients with type 2 diabetes mellitus and atherosclerotic cardiovascular disease. Consider the risks and benefits of ZITUVIMET prior to initiating treatment in patients at risk for heart failure, such as those with a prior history of heart failure and a history of renal impairment, and observe these patients for signs and symptoms of heart failure during therapy. Advise patients of the characteristic symptoms of heart failure and to immediately report such symptoms. If heart failure develops, evaluate and manage according to current standards of care and consider discontinuation of ZITUVIMET.

5.4 Acute Renal Failure

There have been postmarketing reports of worsening renal function, including acute renal failure, sometimes requiring dialysis. Before initiation of therapy with ZITUVIMET and at least annually thereafter, renal function should be assessed. In patients in whom development of renal dysfunction is anticipated, particularly in elderly patients, renal function should be assessed more frequently and ZITUVIMET discontinued if evidence of renal impairment is present. ZITUVIMET is contraindicated in patients with severe renal impairment [see Contraindications (4) and Warnings and Precautions (5.1)].

5.5 Vitamin B12 Deficiency

In controlled clinical trials of metformin of 29 weeks duration, a decrease to subnormal levels of previously normal serum vitamin B12 levels was observed in approximately 7% of patients. Such decrease, possibly due to interference with B12 absorption from the B12-intrinsic factor complex, may be associated with anemia but appears to be rapidly reversible with discontinuation of metformin or vitamin B12 supplementation. Certain individuals (those with inadequate vitamin B12 or calcium intake or absorption) appear to be predisposed to developing subnormal vitamin B12 levels. Measure hematologic parameters on an annual basis and vitamin B12 measurements at 2- to 3-year intervals in patients on ZITUVIMET and manage any abnormalities [see Adverse Reactions (6.1)].

5.6 Hypoglycemia with Concomitant Use with Insulin or Insulin Secretagogues

ZITUVIMET may increase the risk of hypoglycemia when combined with insulin and/or an insulin secretagogue (e.g., sulfonylurea) [see Adverse Reactions (6)]. A lower dose of insulin or insulin secretagogue may be required to minimize the risk of hypoglycemia when used in combination with ZITUVIMET [see Drug Interactions (7)].

5.7 Hypersensitivity Reactions

There have been postmarketing reports of serious hypersensitivity reactions in patients treated with sitagliptin, one of the components of ZITUVIMET. These reactions include anaphylaxis, angioedema, and exfoliative skin conditions including Stevens-Johnson syndrome. Onset of these reactions occurred within the first 3 months after initiation of treatment with sitagliptin, with some reports occurring after the first dose.

If a hypersensitivity reaction is suspected, discontinue ZITUVIMET, assess for other potential causes for the event, and institute alternative treatment for diabetes. [see Adverse Reactions (6.2)].

Angioedema has also been reported with other DPP-4 inhibitors. Use caution in a patient with a history of angioedema with another DPP-4 inhibitor because it is unknown whether such patients will be predisposed to angioedema with ZITUVIMET.

5.8 Severe and Disabling Arthralgia

There have been postmarketing reports of severe and disabling arthralgia in patients taking DPP-4 inhibitors. The time to onset of symptoms following initiation of drug therapy varied from one day to years. Patients experienced relief of symptoms upon discontinuation of the medication. A subset of patients experienced a recurrence of symptoms when restarting the same drug or a different DPP-4 inhibitor. Consider DPP-4 inhibitors as a possible cause for severe joint pain and discontinue drug if appropriate.

5.9 Bullous Pemphigoid

Postmarketing cases of bullous pemphigoid requiring hospitalization have been reported with DPP- 4 inhibitor use. In reported cases, patients typically recovered with topical or systemic immunosuppressive treatment and discontinuation of the DPP-4 inhibitor. Tell patients to report development of blisters or erosions while receiving ZITUVIMET. If bullous pemphigoid is suspected, ZITUVIMET should be discontinued and referral to a dermatologist should be considered for diagnosis and appropriate treatment.

6 ADVERSE REACTIONS

The following adverse reactions are also discussed elsewhere in the prescribing information:

- Lactic Acidosis [see Warnings and Precautions (5.1)]
- Pancreatitis [see Warnings and Precautions (5.2)]
- Heart Failure [see Warnings and Precautions (5.3)]
- Acute Renal Failure [see Warnings and Precautions (5.4)]
- Vitamin B12 Deficiency [see Warnings and Precautions (5.5)]
- Hypoglycemia with Concomitant Use with Insulin or Insulin Secretagogues [see Warnings and Precautions (5.6)]
- Hypersensitivity Reactions [see Warnings and Precautions (5.7)]
- Severe and Disabling Arthralgia [see Warnings and Precautions (5.8)]
- Bullous Pemphigoid [see Warnings and Precautions (5.9)]

6.1 Clinical Trials Experience

Because clinical trials are conducted under widely varying conditions, adverse reaction rates observed in the clinical trials of a drug cannot be directly compared to rates in the clinical trials of another drug and may not reflect the rates observed in practice.

Common Adverse Reactions

Sitagliptin and Metformin Coadministration in Patients with Type 2 Diabetes Mellitus Inadequately Controlled on Diet and Exercise

Table 1 summarizes the most common (≥5% of patients) adverse reactions reported in a 24-week placebo-controlled factorial trial in which sitagliptin and metformin were coadministered to patients with type 2 diabetes mellitus inadequately controlled on diet and exercise.

Table 1: Sitagliptin and Metformin Coadministered to Patients with Type 2 Diabetes Mellitus Inadequately Controlled on Diet and Exercise:
Adverse Reactions Reported in ≥5% of Patients Receiving Combination Therapy (and Greater than in Patients Receiving Placebo) [Intent-to-treat population.]
 | Number of Patients (%)
 | Placebo | Sitagliptin 100 mg once daily | Metformin HCl 500 mg/ Metformin HCl 1,000 mg twice daily [Data pooled for the patients given the lower and higher doses of metformin.] | Sitagliptin 50 mg twice daily + Metformin HCl 500 mg/ Metformin HCl 1,000 mg twice daily
 | N = 176 | N = 179 | N = 364 | N = 372
Diarrhea | 7 (4) | 5 (2.8) | 28 (7.7) | 28 (7.5)
Upper Respiratory Tract Infection | 9 (5.1) | 8 (4.5) | 19 (5.2) | 23 (6.2)
Headache | 5 (2.8) | 2 (1.1) | 14 (3.8) | 22 (5.9)

Sitagliptin Add-on Therapy in Patients with Type 2 Diabetes Mellitus Inadequately Controlled on Metformin Alone

In a 24-week placebo-controlled trial of sitagliptin 100 mg administered once daily added to a twice daily metformin regimen, there were no adverse reactions in ≥5% of patients and more commonly than in patients given placebo. Discontinuation of therapy due to clinical adverse reactions was similar to the placebo treatment group (sitagliptin and metformin, 1.9%; placebo and metformin, 2.5%).

Gastrointestinal Adverse Reactions

The incidences of pre-selected gastrointestinal adverse experiences in patients treated with sitagliptin and metformin were similar to those reported for patients treated with metformin alone. See Table 2.

Table 2: Pre-selected Gastrointestinal Adverse Reactions Reported in Patients with Type 2 Diabetes Mellitus Receiving Sitagliptin and Metformin
 | Number of Patients (%)
 | Trial of Sitagliptin and Metformin in Patients Inadequately Controlled on Diet and Exercise |  |  |  | Trial of Sitagliptin Add-on in Patients Inadequately Controlled on Metformin Alone
 | Placebo | Sitagliptin 100 mg once daily | Metformin HCl 500 mg/ Metformin HCl 1,000 mg twice daily [Data pooled for the patients given the lower and higher doses of metformin.] | Sitagliptin 50 mg twice daily + Metformin HCl 500 mg/ Metformin HCl 1,000 mg twice daily | Placebo and Metformin HCl ≥1,500 mg daily | Sitagliptin 100 mg once daily and Metformin HCl ≥1,500 mg daily
 | N = 176 | N = 179 | N = 364 | N = 372 | N = 237 | N = 464
Diarrhea | 7 (4) | 5 (2.8) | 28 (7.7) | 28 (7.5) | 6 (2.5) | 11 (2.4)
Nausea | 2 (1.1) | 2 (1.1) | 20 (5.5) | 18 (4.8) | 2 (0.8) | 6 (1.3)
Vomiting | 1 (0.6) | 0 (0) | 2 (0.5) | 8 (2.2) | 2 (0.8) | 5 (1.1)
Abdominal Pain [Abdominal discomfort was included in the analysis of abdominal pain in the trial of initial therapy.] | 4 (2.3) | 6 (3.4) | 14 (3.8) | 11 (3) | 9 (3.8) | 10 (2.2)

Sitagliptin in Combination with Metformin and Glimepiride

In a 24-week placebo-controlled trial of sitagliptin 100 mg as add-on therapy in patients with type 2 diabetes mellitus inadequately controlled on metformin and glimepiride (sitagliptin, N=116; placebo, N=113), the adverse reactions reported in ≥5% of patients treated with sitagliptin and more commonly than in patients treated with placebo were: hypoglycemia (see Table 3) and headache (6.9%, 2.7%).

Sitagliptin in Combination with Metformin and Rosiglitazone

In a placebo-controlled trial of sitagliptin 100 mg as add-on therapy in patients with type 2 diabetes mellitus inadequately controlled on metformin and rosiglitazone (sitagliptin, N=181; placebo, N=97), the adverse reactions reported through Week 18 in ≥5% of patients treated with sitagliptin and more commonly than in patients treated with placebo were: upper respiratory tract infection (sitagliptin, 5.5%; placebo, 5.2%) and nasopharyngitis (6.1%, 4.1%). Through Week 54, the adverse reactions reported in ≥5% of patients treated with sitagliptin and more commonly than in patients treated with placebo were: upper respiratory tract infection (sitagliptin, 15.5%; placebo, 6.2%), nasopharyngitis (11%, 9.3%), peripheral edema (8.3%, 5.2%), and headache (5.5%, 4.1%).

Sitagliptin in Combination with Metformin and Insulin

In a 24-week placebo-controlled trial of sitagliptin 100 mg as add-on therapy in patients with type 2 diabetes mellitus inadequately controlled on metformin and insulin (sitagliptin, N=229; placebo, N=233), the only adverse reaction reported in ≥5% of patients treated with sitagliptin and more commonly than in patients treated with placebo was hypoglycemia (Table 3).

Hypoglycemia

In the above trials (N=5), adverse reactions of hypoglycemia were based on all reports of symptomatic hypoglycemia; a concurrent glucose measurement was not required although most (77%) reports of hypoglycemia were accompanied by a blood glucose measurement ≤70 mg/dL. When the combination of sitagliptin and metformin was coadministered with a sulfonylurea or with insulin, the percentage of patients reporting at least one adverse reaction of hypoglycemia was higher than that observed with placebo and metformin coadministered with a sulfonylurea or with insulin (Table 3).

Table 3: Incidence and Rate of Hypoglycemia [Adverse reactions of hypoglycemia were based on all reports of symptomatic hypoglycemia; a concurrent glucose measurement was not required: Intent-to-treat population.] in Placebo-Controlled Clinical Trials of Sitagliptin in Combination with Metformin Coadministered with Glimepiride or Insulin
Add-On to Glimepiride + Metformin (24 weeks) | Sitagliptin 100 mg + Metformin + Glimepiride | Placebo + Metformin + Glimepiride
 | N = 116 | N = 113
Overall (%) | 19 (16.4) | 1 (0.9)
Rate (episodes/patient-year) [Based on total number of events (i.e., a single patient may have had multiple events).] | 0.82 | 0.02
Severe (%) [Severe events of hypoglycemia were defined as those events requiring medical assistance or exhibiting depressed level/loss of consciousness or seizure.] | 0 (0) | 0 (0)
Add-On to Insulin + Metformin (24 weeks) | Sitagliptin 100 mg + Metformin + Insulin | Placebo + Metformin + Insulin
 | N = 229 | N = 233
Overall (%) | 35 (15.3) | 19 (8.2)
Rate (episodes/patient-year) | 0.98 | 0.61
Severe (%) | 1 (0.4) | 1 (0.4)

The overall incidence of reported adverse reactions of hypoglycemia in patients with type 2 diabetes mellitus inadequately controlled on diet and exercise was 0.6% in patients given placebo, 0.6% in patients given sitagliptin alone, 0.8% in patients given metformin alone, and 1.6% in patients given sitagliptin in combination with metformin. In patients with type 2 diabetes mellitus inadequately controlled on metformin alone, the overall incidence of adverse reactions of hypoglycemia was 1.3% in patients given add-on sitagliptin and 2.1% in patients given add-on placebo.

In the trial of sitagliptin and add-on combination therapy with metformin and rosiglitazone, the overall incidence of hypoglycemia was 2.2% in patients given add-on sitagliptin and 0% in patients given add-on placebo through Week 18. Through Week 54, the overall incidence of hypoglycemia was 3.9% in patients given add-on sitagliptin and 1% in patients given add-on placebo.

In an additional, 30-week placebo-controlled, trial of patients with type 2 diabetes mellitus inadequately controlled with metformin comparing the maintenance of sitagliptin 100 mg versus withdrawal of sitagliptin when initiating basal insulin therapy, the event rate and incidence of documented symptomatic hypoglycemia (blood glucose measurement ≤70 mg/dL) did not differ between the sitagliptin and placebo groups.

Vital Signs and Electrocardiograms

With the combination of sitagliptin and metformin, no clinically meaningful changes in vital signs or in ECG (including in QTc interval) were observed.

Pancreatitis

In a pooled analysis of 19 double-blind clinical trials that included data from 10,246 patients randomized to receive sitagliptin 100 mg/day (N=5,429) or corresponding (active or placebo) control (N=4,817), the incidence of acute pancreatitis was 0.1 per 100 patient-years in each group (4 patients with an event in 4,708 patient-years for sitagliptin and 4 patients with an event in 3,942 patient-years for control).

Sitagliptin

The most common adverse experience in sitagliptin monotherapy reported in ≥5% of patients and more commonly than in patients given placebo was nasopharyngitis.

Metformin

The most common (>5%) established adverse reactions due to initiation of metformin therapy are diarrhea, nausea/vomiting, flatulence, abdominal discomfort, indigestion, asthenia, and headache.

Laboratory Tests

Sitagliptin

The incidence of laboratory adverse reactions was similar in patients treated with sitagliptin and metformin (7.6%) compared to patients treated with placebo and metformin (8.7%). In most but not all trials, a small increase in white blood cell count (approximately 200 cells/microL difference in WBC vs placebo; mean baseline WBC approximately 6,600 cells/microL) was observed due to a small increase in neutrophils. This change in laboratory parameters is not considered to be clinically relevant.

Metformin

In controlled clinical trials of metformin of 29 weeks duration, a decrease to subnormal levels of previously normal serum vitamin B12 levels, without clinical manifestations, was observed in approximately 7% of patients. Such decrease, possibly due to interference with B12 absorption from the B12-intrinsic factor complex, is, however, very rarely associated with anemia and appears to be rapidly reversible with discontinuation of metformin or vitamin B12 supplementation.

6.2 Postmarketing Experience

Additional adverse reactions have been identified during postapproval use of ZITUVIMET, sitagliptin, or metformin. Because these reactions are reported voluntarily from a population of uncertain size, it is generally not possible to reliably estimate their frequency or establish a causal relationship to drug exposure.

Skin and subcutaneous tissue disorders: hypersensitivity reactions including anaphylaxis, angioedema, rash, urticaria, cutaneous vasculitis, and exfoliative skin conditions including Stevens-Johnson syndrome; bullous pemphigoid;

Respiratory, thoracic and mediastinal disorders: upper respiratory tract infection;

Hepatobiliary disorders: hepatic enzyme elevations; cholestatic, hepatocellular, and mixed hepatocellular liver injury;

Gastrointestinal disorders: acute pancreatitis, including fatal and non-fatal hemorrhagic and necrotizing pancreatitis [see Indications and Usage (1)]; constipation; vomiting; mouth ulceration; stomatitis;

Renal and urinary disorders: worsening renal function, including acute renal failure (sometimes requiring dialysis) and tubulointerstitial nephritis;

Musculoskeletal and connective tissue disorders: severe and disabling arthralgia; myalgia; pain in extremity; back pain; pruritus; rhabdomyolysis;

Nervous system disorders: headache.

7 DRUG INTERACTIONS

Table 4 presents clinically significant drug interactions with ZITUVIMET:

Table 4: Clinically Significant Drug Interactions with ZITUVIMET
Carbonic Anhydrase Inhibitors
Clinical Impact: | Carbonic anhydrase inhibitors frequently cause a decrease in serum bicarbonate and induce non-anion gap, hyperchloremic metabolic acidosis. Concomitant use of these drugs with ZITUVIMET may increase the risk for lactic acidosis.
Intervention: | Consider more frequent monitoring of these patients.
Examples: | Topiramate, zonisamide, acetazolamide or dichlorphenamide.
Drugs that Reduce Metformin Clearance
Clinical Impact: | Concomitant use of drugs that interfere with common renal tubular transport systems involved in the renal elimination of metformin (e.g., organic cationic transporter-2 [OCT2] / multidrug and toxin extrusion [MATE] inhibitors) could increase systemic exposure to metformin and may increase the risk for lactic acidosis [see Clinical Pharmacology (12.3)].
Intervention: | Consider the benefits and risks of concomitant use with ZITUVIMET.
Examples: | Ranolazine, vandetanib, dolutegravir, and cimetidine.
Alcohol
Clinical Impact: | Alcohol is known to potentiate the effect of metformin on lactate metabolism.
Intervention: | Warn patients against alcohol intake while receiving ZITUVIMET.
Insulin Secretagogues or Insulin
Clinical Impact: | Coadministration of ZITUVIMET with an insulin secretagogue (e.g., sulfonylurea) or insulin may increase the risk of hypoglycemia.
Intervention: | Patients receiving an insulin secretagogue or insulin may require lower doses of the insulin secretagogue or insulin.
Drugs Affecting Glycemic Control
Clinical Impact: | Certain drugs tend to produce hyperglycemia and may lead to loss of glycemic control.
Intervention: | When such drugs are administered to a patient receiving ZITUVIMET, observe the patient closely for loss of blood glucose control. When such drugs are withdrawn from a patient receiving ZITUVIMET, observe the patient closely for hypoglycemia.
Examples: | Thiazides and other diuretics, corticosteroids, phenothiazines, thyroid products, estrogens, oral contraceptives, phenytoin, nicotinic acid, sympathomimetics, calcium channel blockers, and isoniazid.

8 USE IN SPECIFIC POPULATIONS

8.1 Pregnancy

Risk Summary

Available data with ZITUVIMET and sitagliptin use in pregnant women are not sufficient to inform a ZITUVIMET-associated or sitagliptin-associated risk for major birth defects and miscarriage. Published studies with metformin use during pregnancy have not reported a clear association with metformin and major birth defect or miscarriage risk [see Data]. There are risks to the mother and fetus associated with poorly controlled diabetes in pregnancy [see Clinical Considerations]. No adverse developmental effects were observed when sitagliptin was administered to pregnant rats and rabbits during organogenesis at oral doses up to 30-times and 20-times, respectively, the 100 mg clinical dose, based on AUC. No adverse developmental effects were observed when metformin was administered to pregnant Sprague Dawley rats and rabbits during organogenesis at doses up to 2- and 6-times, respectively, a 2,000 mg clinical dose, based on body surface area [see Data].

The estimated background risk of major birth defects is 6 to 10% in women with pre-gestational diabetes with a hemoglobin A1c (A1C) >7% and has been reported to be as high as 20% to 25% in women with a A1C >10%. In the U.S. general population, the estimated background risk of major birth defects and miscarriage in clinically recognized pregnancies is 2% to 4% and 15% to 20% respectively.

Clinical Considerations

Disease-Associated Maternal and/or Embryo/Fetal Risk

Poorly controlled diabetes in pregnancy increases the maternal risk for diabetic ketoacidosis, preeclampsia, spontaneous abortions, preterm delivery, and delivery complications. Poorly controlled diabetes increases the fetal risk for major birth defects, still birth, and macrosomia related morbidity.

Data

Human Data

Published data from post-marketing studies do not report a clear association with metformin and major birth defects, miscarriage, or adverse maternal or fetal outcomes when metformin is used during pregnancy. However, these studies cannot definitely establish the absence of any risk because of methodological limitations, including small sample size and inconsistent comparator groups.

Animal Data

Sitagliptin and Metformin

No animal reproduction studies were conducted with the coadministration of sitagliptin and metformin.

Sitagliptin

In embryo-fetal development studies, sitagliptin administered to pregnant rats and rabbits during organogenesis (gestation day 6 to 20) did not adversely affect developmental outcomes at oral doses up to 250 mg/kg (30-times the 100 mg clinical dose) and 125 mg/kg (20-times the 100 mg clinical dose), respectively, based on AUC. Higher doses in rats associated with maternal toxicity increased the incidence of rib malformations in offspring at 1,000 mg/kg, or approximately 100-times the clinical dose, based on AUC. Placental transfer of sitagliptin was observed in pregnant rats and rabbits.

Sitagliptin administered to female rats from gestation day 6 to lactation day 21 caused no functional or behavioral toxicity in offspring of rats at doses up to 1,000 mg/kg.

Metformin

Metformin did not cause adverse developmental effects when administered to pregnant Sprague Dawley rats and rabbits up to 600 mg/kg/day during the period of organogenesis. This represents an exposure of about 2- and 6-times a 2,000 mg clinical dose based on body surface area (mg/m^2) for rats and rabbits, respectively.

8.2 Lactation

Risk Summary

There is no information regarding the presence of ZITUVIMET in human milk, the effects on the breastfed infant, or the effects on milk production. Limited published studies report that metformin is present in human milk [see Data]. There are no reports of adverse effects on breastfed infants exposed to metformin. There is no information on the effects of metformin on milk production. Sitagliptin is present in rat milk and therefore possibly present in human milk [see Data]. The developmental and health benefits of breastfeeding should be considered along with the mother's clinical need for ZITUVIMET and any potential adverse effects on the breastfed infant from ZITUVIMET or from the underlying maternal condition.

Data

Sitagliptin

Sitagliptin is secreted in the milk of lactating rats at a milk to plasma ratio of 4:1.

Metformin

Published clinical lactation studies report that metformin is present in human milk, which resulted in infant doses approximately 0.11% to 1% of the maternal weight-adjusted dosage and a milk/plasma ratio ranging between 0.13 and 1. However, the studies were not designed to definitely establish the risk of use of metformin during lactation because of small sample size and limited adverse event data collected in infants.

8.3 Females and Males of Reproductive Potential

Discuss the potential for unintended pregnancy with premenopausal women as therapy with metformin may result in ovulation in some anovulatory women.

8.4 Pediatric Use

The safety and effectiveness of ZITUVIMET have not been established in pediatric patients.

Pediatric information describing clinical studies in which efficacy was not demonstrated is approved for Merck Sharp and Dohme's JANUMET (sitagliptin and metformin hydrochloride) tablets. However, due to Merck Sharp and Dohme's marketing exclusivity rights, this drug product is not labeled with that information.

8.5 Geriatric Use

ZITUVIMET

In general, dose selection for an elderly patient should be cautious, usually starting at the low end of the dosing range, reflecting the greater frequency of decreased hepatic, renal, or cardiac function, and of concomitant disease or other drug therapy and the higher risk of lactic acidosis. Renal function should be assessed more frequently in elderly patients. [See Contraindications (4); Warnings and Precautions (5.1, 5.4) and Clinical Pharmacology (12.3).]

Sitagliptin

Of the total number of subjects (N=3,884) in clinical studies of sitagliptin, 725 patients were 65 years and over, while 61 patients were 75 years and over. No overall differences in safety or effectiveness of sitagliptin have been observed between subjects 65 years and over and younger patients.

Metformin

Controlled clinical studies of metformin did not include sufficient numbers of elderly patients to determine whether they respond differently from younger patients, although other reported clinical experience has not identified differences in responses between the elderly and young patients.

8.6 Renal Impairment

ZITUVIMET

ZITUVIMET is not recommended in patients with an eGFR between 30 and less than 45 mL/min/1.73 m^2 because these patients require a lower dosage of sitagliptin than what is available in the fixed dose combination ZITUVIMET product. ZITUVIMET is contraindicated in severe renal impairment, patients with an eGFR below 30 mL/min/1.73 m^2 [see Dosage and Administration (2.2) >, Contraindications (4)>, Warnings and Precautions (5.1)> and Clinical Pharmacology (12.3)].

Sitagliptin

Sitagliptin is excreted by the kidney, and sitagliptin exposure is increased in patients with renal impairment. [see Clinical Pharmacology (12.3)].

Metformin

Metformin is substantially excreted by the kidney, and the risk of metformin accumulation and lactic acidosis increases with the degree of renal impairment.

8.7 Hepatic Impairment

Use of metformin in patients with hepatic impairment has been associated with some cases of lactic acidosis. ZITUVIMET is not recommended in patients with hepatic impairment. [see Warnings and Precautions (5.1)].

10 OVERDOSAGE

In the event of overdose with ZITUVIMET, consider contacting the Poison Help Line (1-800-222-1222) or a medical toxicologist for additional overdosage management recommendations. Employ the usual supportive measures dictated by the patient's clinical status. Per clinical judgement, consider removal of unabsorbed material from the gastrointestinal tract, and clinical monitoring (including obtaining an ECG).

Sitagliptin is modestly dialyzable. In clinical studies, approximately 13.5% of the dose was removed over a 3- to 4-hour hemodialysis session. Prolonged hemodialysis may be considered if clinically appropriate. It is not known if sitagliptin is dialyzable by peritoneal dialysis.

Overdose of metformin has occurred, including ingestion of amounts greater than 50 grams. Hypoglycemia was reported in approximately 10% of cases, but no causal association with metformin has been established. Lactic acidosis has been reported in approximately 32% of metformin overdose cases [see Warnings and Precautions (5.1)]. Metformin is dialyzable with a clearance of up to 170 mL/min under good hemodynamic conditions. Therefore, hemodialysis may be useful for removal of accumulated drug from patients in whom metformin overdosage is suspected.

11 DESCRIPTION

ZITUVIMET (sitagliptin and metformin HCl) tablets for oral use contain sitagliptin and metformin HCl.

Sitagliptin

Sitagliptin is an orally-active inhibitor of DPP-4 enzyme. Sitagliptin is present in ZITUVIMET tablets in the form of sitagliptin free base. Sitagliptin free base is described chemically as 7-[(3R)-3-amino-1-oxo-4-(2,4,5-trifluorophenyl)butyl]-5,6,7,8-tetrahydro-3 (trifluoromethyl)-1,2,4-triazolo[4,3-a]pyrazine with an empirical formula of C16H15F6N5O and a molecular weight of 407.31. The structural formula is:

Sitagliptin free base is a white to off-white, non-hygroscopic powder. It is soluble in methanol and slightly soluble in water.

Metformin HCl USP

Metformin HCl, USP (N,N-dimethylimidodicarbonimidic diamide hydrochloride) is not chemically or pharmacologically related to any other classes of oral antihyperglycemic agents. Metformin HCl, USP is a white crystalline powder with a molecular formula of C4H11N5•HCl and a molecular weight of 165.62. Metformin HCl is freely soluble in water, slightly soluble in ethanol (95%), practically insoluble in acetone and in methylene chloride. The pKa of metformin HCl is 12.4. The pH of a 1% aqueous solution of metformin HCl is 6.68.

The structural formula is as shown:

ZITUVIMET is available as film-coated tablets containing:

- 50 mg of sitagliptin and 389.93 mg of metformin equivalent to 500 mg metformin HCl (ZITUVIMET 50/500).
- 50 mg of sitagliptin and 779.86 mg of metformin equivalent to 1,000 mg metformin HCl (ZITUVIMET 50/1,000).

Each film-coated tablet of ZITUVIMET contains the following inactive ingredients: colloidal silicon dioxide, croscarmellose sodium, low substituted hydroxypropylcellulose, magnesium stearate, malic acid, microcrystalline cellulose, povidone, and sodium stearyl fumarate. In addition, the film coating contains the following inactive ingredients: polyethylene glycol, polyvinyl alcohol, talc, and titanium dioxide. The film coating of 50 mg/1,000 mg also contains: FD&C yellow #6 aluminum lake, iron oxide red, and iron oxide yellow.

12 CLINICAL PHARMACOLOGY

12.1 Mechanism of Action

ZITUVIMET

ZITUVIMET combines two antihyperglycemic agents with complementary mechanisms of action to improve glycemic control in patients with type 2 diabetes mellitus: sitagliptin, a DPP- 4 inhibitor, and metformin HCl, a member of the biguanide class.

Sitagliptin

Sitagliptin is a DPP-4 inhibitor, which is believed to exert its actions in patients with type 2 diabetes mellitus by slowing the inactivation of incretin hormones. Concentrations of the active intact hormones are increased by sitagliptin, thereby increasing and prolonging the action of these hormones. Incretin hormones, including glucagon-like peptide-1 (GLP-1) and glucose-dependent insulinotropic polypeptide (GIP), are released by the intestine throughout the day, and levels are increased in response to a meal. These hormones are rapidly inactivated by the enzyme DPP-4. The incretins are part of an endogenous system involved in the physiologic regulation of glucose homeostasis. When blood glucose concentrations are normal or elevated, GLP-1 and GIP increase insulin synthesis and release from pancreatic beta cells by intracellular signaling pathways involving cyclic AMP. GLP-1 also lowers glucagon secretion from pancreatic alpha cells, leading to reduced hepatic glucose production. By increasing and prolonging active incretin levels, sitagliptin increases insulin release and decreases glucagon levels in the circulation in a glucose-dependent manner. Sitagliptin demonstrates selectivity for DPP-4 and does not inhibit DPP-8 or DPP-9 activity in vitro at concentrations approximating those from therapeutic doses.

Metformin

Metformin is an antihyperglycemic agent which improves glucose tolerance in patients with type 2 diabetes mellitus, lowering both basal and postprandial plasma glucose. Metformin decreases hepatic glucose production, decreases intestinal absorption of glucose, and improves insulin sensitivity by increasing peripheral glucose uptake and utilization. With metformin therapy, insulin secretion remains unchanged while fasting insulin levels and day-long plasma insulin response may decrease.

12.2 Pharmacodynamics

Sitagliptin

In patients with type 2 diabetes mellitus, administration of sitagliptin led to inhibition of DPP-4 enzyme activity for a 24-hour period. After an oral glucose load or a meal, this DPP-4 inhibition resulted in a 2- to 3-fold increase in circulating levels of active GLP-1 and GIP, decreased glucagon concentrations, and increased responsiveness of insulin release to glucose, resulting in higher C-peptide and insulin concentrations. The rise in insulin with the decrease in glucagon was associated with lower fasting glucose concentrations and reduced glucose excursion following an oral glucose load or a meal.

In studies with healthy subjects, sitagliptin did not lower blood glucose or cause hypoglycemia.

Sitagliptin and Metformin Coadministration

In a two-day study in healthy subjects, sitagliptin alone increased active GLP-1 concentrations, whereas metformin alone increased active and total GLP-1 concentrations to similar extents. Coadministration of sitagliptin and metformin had an additive effect on active GLP-1 concentrations. Sitagliptin, but not metformin, increased active GIP concentrations. It is unclear what these findings mean for changes in glycemic control in patients with type 2 diabetes mellitus.

Cardiac Electrophysiology

In a randomized, placebo-controlled crossover study, 79 healthy subjects were administered a single oral dose of sitagliptin 100 mg, sitagliptin 800 mg (8 times the recommended dose), and placebo. At the recommended dose of 100 mg, there was no effect on the QTc interval obtained at the peak plasma concentration, or at any other time during the study. Following the 800-mg dose, the maximum increase in the placebo-corrected mean change in QTc from baseline at 3 hours postdose was 8.0 msec. This increase is not considered to be clinically significant. At the 800-mg dose, peak sitagliptin plasma concentrations were approximately 11 times higher than the peak concentrations following a 100-mg dose.

In patients with type 2 diabetes mellitus administered sitagliptin 100 mg (N=81) or sitagliptin 200 mg (N=63) daily, there were no meaningful changes in QTc interval based on ECG data obtained at the time of expected peak plasma concentration.

12.3 Pharmacokinetics

Sitagliptin

The pharmacokinetics of sitagliptin have been extensively characterized in healthy subjects and patients with type 2 diabetes mellitus. Following a single oral 100-mg dose to healthy volunteers, mean plasma AUC of sitagliptin was 8.52 µM•hr, Cmax was 950 nM, and apparent terminal half-life (t1/2) was 12.4 hours. Plasma AUC of sitagliptin increased in a dose-proportional manner and increased approximately 14% following 100 mg doses at steady-state compared to the first dose. The intra-subject and inter-subject coefficients of variation for sitagliptin AUC were small (5.8% and 15.1%). The pharmacokinetics of sitagliptin was generally similar in healthy subjects and in patients with type 2 diabetes mellitus.

Absorption

Sitagliptin

After oral administration of a 100 mg dose to healthy subjects, sitagliptin was rapidly absorbed with peak plasma concentrations (median Tmax) occurring 1 to 4 hours postdose. The absolute bioavailability of sitagliptin is approximately 87%.

Effect of Food

Coadministration of a high-fat meal with sitagliptin had no effect on the pharmacokinetics of sitagliptin.

Metformin

The absolute bioavailability of a metformin HCl 500-mg tablet given under fasting conditions is approximately 50% to 60%. Studies using single oral doses of metformin HCl tablets 500 mg to 1,500 mg, and 850 mg to 2,550 mg (approximately 1.3 times the maximum recommended daily dosage), indicate that there is a lack of dose proportionality with increasing doses, which is due to decreased absorption rather than an alteration in elimination.

Effect of Food

Food decreases the extent of and slightly delays the absorption of metformin, as shown by approximately a 40% lower mean peak plasma concentration (Cmax), a 25% lower area under the plasma concentration versus time curve (AUC), and a 35-minute prolongation of time to peak plasma concentration (Tmax) following administration of a single 850-mg tablet of metformin HCl with food, compared to the same tablet strength administered fasting. The clinical relevance of these decreases is unknown.

Distribution

Sitagliptin

The mean volume of distribution at steady state following a single 100-mg intravenous dose of sitagliptin to healthy subjects is approximately 198 liters. The fraction of sitagliptin reversibly bound to plasma proteins is low (38%).

Metformin

The apparent volume of distribution (V/F) of metformin following single oral doses of metformin HCl tablets 850 mg averaged 654 ± 358 L. Metformin is negligibly bound to plasma proteins, in contrast to sulfonylureas, which are more than 90% protein bound. Metformin partitions into erythrocytes, most likely as a function of time. At usual clinical doses and dosing schedules of metformin HCl tablets, steady-state plasma concentrations of metformin are reached within 24 to 48 hours and are generally <1 mcg/mL.

Elimination

Sitagliptin

Approximately 79% of sitagliptin is excreted unchanged in the urine with metabolism being a minor pathway of elimination. The apparent terminal t1/2 following a 100 mg oral dose of sitagliptin was approximately 12.4 hours and renal clearance was approximately 350 mL/min.

Metformin

Following oral administration, approximately 90% of the absorbed drug is eliminated via the renal route within the first 24 hours, with a plasma elimination half-life of approximately 6.2 hours. In blood, the elimination half-life is approximately 17.6 hours, suggesting that the erythrocyte mass may be a compartment of distribution.

Metabolism

Sitagliptin

Following a [^14C] sitagliptin oral dose, approximately 16% of the radioactivity was excreted as metabolites of sitagliptin. Six metabolites were detected at trace levels and are not expected to contribute to the plasma DPP-4 inhibitory activity of sitagliptin. In vitro studies indicated that the primary enzyme responsible for the limited metabolism of sitagliptin was CYP3A4, with contribution from CYP2C8.

Metformin

Intravenous single-dose studies in normal subjects demonstrate that metformin is excreted unchanged in the urine and does not undergo hepatic metabolism (no metabolites have been identified in humans) nor biliary excretion.

Excretion

Sitagliptin

Following administration of an oral [^14C] sitagliptin dose to healthy subjects, approximately 100% of the administered radioactivity was eliminated in feces (13%) or urine (87%) within one week of dosing.

Elimination of sitagliptin occurs primarily via renal excretion and involves active tubular secretion. Sitagliptin is a substrate for human organic anion transporter-3 (hOAT-3), which may be involved in the renal elimination of sitagliptin. The clinical relevance of hOAT-3 in sitagliptin transport has not been established. Sitagliptin is also a substrate of p-glycoprotein (P-gp), which may also be involved in mediating the renal elimination of sitagliptin. However, cyclosporine, a P-gp inhibitor, did not reduce the renal clearance of sitagliptin.

Metformin

Elimination of metformin occurs primarily via renal excretion. Renal clearance is approximately 3.5 times greater than creatinine clearance, which indicates that tubular secretion is the major route of metformin elimination.

Specific Populations

Patients with Renal Impairment

ZITUVIMET

Studies characterizing the pharmacokinetics of sitagliptin and metformin after administration of ZITUVIMET in renally impaired patients have not been performed [see Dosage and Administration (2.2)].

Sitagliptin

An approximately 2-fold increase in the plasma AUC of sitagliptin was observed in patients with moderate renal impairment with eGFR of 30 to less than 45 mL/min/1.73 m^2, and an approximately 4-fold increase was observed in patients with severe renal impairment including patients with end-stage renal disease (ESRD) on hemodialysis, as compared to normal healthy control subjects. [see Dosage and Administration (2.2)].

Metformin

In patients with decreased renal function, the plasma and blood half-life of metformin is prolonged and the renal clearance is decreased [see Contraindications (4) and Warnings and Precautions (5.1)].

Patients with Hepatic Impairment

ZITUVIMET

Studies characterizing the pharmacokinetics of sitagliptin and metformin after administration of ZITUVIMET in patients with hepatic impairment have not been performed.

Sitagliptin

In patients with moderate hepatic impairment (Child-Pugh score 7 to 9), mean AUC and Cmax of sitagliptin increased approximately 21% and 13%, respectively, compared to healthy matched controls following administration of a single 100-mg dose of sitagliptin. These differences are not considered to be clinically meaningful. There is no clinical experience in patients with severe hepatic impairment (Child-Pugh score >9) [see Use in Specific Populations (8.7)].

Metformin

No pharmacokinetic studies of metformin have been conducted in patients with hepatic impairment.

Effects of Age, Body Mass Index (BMI), Gender, and Race

Sitagliptin

Based on a population pharmacokinetic analysis or a composite analysis of available pharmacokinetic data, BMI, gender, and race do not have a clinically meaningful effect on the pharmacokinetics of sitagliptin. When the effects of age on renal function are taken into account, age alone did not have a clinically meaningful impact on the pharmacokinetics of sitagliptin based on a population pharmacokinetic analysis. Elderly subjects (65 to 80 years) had approximately 19% higher plasma concentrations of sitagliptin compared to younger subjects.

Metformin

Limited data from controlled pharmacokinetic studies of metformin in healthy elderly subjects suggest that total plasma clearance of metformin is decreased, the half-life is prolonged, and Cmax is increased, compared to healthy young subjects. From these data, it appears that the change in metformin pharmacokinetics with aging is primarily accounted for by a change in renal function.

Metformin pharmacokinetic parameters did not differ significantly between normal subjects and patients with type 2 diabetes mellitus when analyzed according to gender. Similarly, in controlled clinical studies in patients with type 2 diabetes mellitus, the antihyperglycemic effect of metformin was comparable in males and females.

No studies of metformin pharmacokinetic parameters according to race have been performed. In controlled clinical studies of metformin in patients with type 2 diabetes mellitus, the antihyperglycemic effect was comparable in Whites (n=249), Blacks or African Americans (n=51), and Hispanics (n=24).

Drug Interaction Studies

ZITUVIMET

Coadministration of multiple doses of sitagliptin (50 mg) and metformin HCl (1,000 mg) given twice daily did not meaningfully alter the pharmacokinetics of either sitagliptin or metformin in patients with type 2 diabetes mellitus.

Pharmacokinetic drug interaction studies with ZITUVIMET have not been performed; however, such studies have been conducted with the individual components of ZITUVIMET (sitagliptin and metformin HCl).

Sitagliptin

In Vitro Assessment of Drug Interactions

Sitagliptin is not an inhibitor of CYP isozymes CYP3A4, 2C8, 2C9, 2D6, 1A2, 2C19 or 2B6, and is not an inducer of CYP3A4. Sitagliptin is a P-gp substrate but does not inhibit P-gp mediated transport of digoxin. Based on these results, sitagliptin is considered unlikely to cause interactions with other drugs that utilize these pathways.

Sitagliptin is not extensively bound to plasma proteins. Therefore, the propensity of sitagliptin to be involved in clinically meaningful drug-drug interactions mediated by plasma protein binding displacement is very low.

In Vivo Assessment of Drug Interactions

Effects of Sitagliptin on Other Drugs

In clinical studies, sitagliptin did not meaningfully alter the pharmacokinetics of metformin, glyburide, simvastatin, rosiglitazone, digoxin, warfarin, or an oral contraception (ethinyl estradiol and norethindrone) (Table 5), providing in vivo evidence of a low propensity for causing drug interactions with substrates of CYP3A4, CYP2C8, CYP2C9, P-gp, and organic cationic transporter (OCT).

Table 5: Effect of Sitagliptin on Systemic Exposure of Coadministered Drugs
Coadministered Drug | Dose of Coadministered Drug [All doses administered as single dose unless otherwise specified.] | Dose of Sitagliptin | Geometric Mean Ratio (ratio with/without sitagliptin) No Effect = 1
Coadministered Drug | Dose of Coadministered Drug [All doses administered as single dose unless otherwise specified.] | Dose of Sitagliptin |  | AUC [AUC is reported as AUC0-∞ unless otherwise specified.] | Cmax
Digoxin | 0.25 mg‡ once daily for 10 days | 100 mg [Multiple dose.] once daily for 10 days | Digoxin | 1.11 [AUC0-24hr.] | 1.18
Glyburide | 1.25 mg | 200 mg once daily for 6 days | Glyburide | 1.09 | 1.01
Simvastatin | 20 mg | 200 mg once daily for 5 days | Simvastatin | 0.85 [AUC0-last.] | 0.8
Simvastatin | 20 mg | 200 mg once daily for 5 days | Simvastatin Acid | 1.12 | 1.06
Rosiglitazone | 4 mg | 200 mg once daily for 5 days | Rosiglitazone | 0.98 | 0.99
Warfarin | 30 mg single dose on day 5 | 200 mg once daily for 11 days | S(-) Warfarin | 0.95 | 0.89
Warfarin | 30 mg single dose on day 5 | 200 mg once daily for 11 days | R(+) Warfarin | 0.99 | 0.89
Ethinyl estradiol and norethindrone | 21 days once daily of 35 µg ethinyl estradiol with norethindrone 0.5 mg x 7 days, 0.75 mg x 7 days, 1 mg x 7 days | 200 mg once daily for 21 days | Ethinyl estradiol | 0.99 | 0.97
Ethinyl estradiol and norethindrone | 21 days once daily of 35 µg ethinyl estradiol with norethindrone 0.5 mg x 7 days, 0.75 mg x 7 days, 1 mg x 7 days | 200 mg once daily for 21 days | Norethindrone | 1.03 | 0.98
Metformin HCl | 1,000 mg twice daily for 14 days | 50 mg twice daily for 7 days | Metformin | 1.02 [AUC0-12hr.] | 0.97

Effects of Other Drugs on Sitagliptin

Clinical data described below suggest that sitagliptin is not susceptible to clinically meaningful interactions by coadministered medications (Table 6).

Table 6: Effect of Coadministered Drugs on Systemic Exposure of Sitagliptin
Coadministered Drug | Dose of Coadministered Drug [All doses administered as single dose unless otherwise specified.] | Dose of Sitagliptin | Geometric Mean Ratio (ratio with/without coadministered drug) No Effect = 1
Coadministered Drug | Dose of Coadministered Drug [All doses administered as single dose unless otherwise specified.] | Dose of Sitagliptin |  | AUC [AUC is reported as AUC0-∞ unless otherwise specified.] | Cmax
Cyclosporine | 600 mg once daily | 100 mg once daily | Sitagliptin | 1.29 | 1.68
Metformin HCl | 1,000 mg [Multiple dose.] twice daily for 14 days | 50 mg twice daily for 7 days | Sitagliptin | 1.02 [AUC0-12hr.] | 1.05

Metformin HCl

Table 7: Effect of Metformin HCl on Systemic Exposure of Coadministered Drugs
Coadministered Drug | Dose of Coadministered Drug [All doses administered as single dose unless otherwise specified.] | Dose of Metformin HCl | Geometric Mean Ratio (ratio with/without metformin) No Effect = 1
Coadministered Drug | Dose of Coadministered Drug [All doses administered as single dose unless otherwise specified.] | Dose of Metformin HCl |  | AUC [AUC is reported as AUC0-∞ unless otherwise specified.] | Cmax
Cimetidine | 400 mg | 850 mg | Cimetidine | 0.95 [AUC0-24hr.] | 1.01
Glyburide | 5 mg | 500 mg [GLUMETZA (metformin HCl extended-release tablets) 500 mg.] | Glyburide | 0.78 [Ratio of arithmetic means, p value of difference <0.05.] | 0.63
Furosemide | 40 mg | 850 mg | Furosemide | 0.87 | 0.69
Nifedipine | 10 mg | 850 mg | Nifedipine | 1.10 | 1.08
Propranolol | 40 mg | 850 mg | Propranolol | 1.01 | 0.94
Ibuprofen | 400 mg | 850 mg | Ibuprofen | 0.97 [Ratio of arithmetic means.] | 1.01

Table 8: Effect of Coadministered Drugs on Systemic Exposure of Metformin HCl
Coadministered Drug | Dose of Coadministered Drug [All doses administered as single dose unless otherwise specified.] | Dose of Metformin HCl | Geometric Mean Ratio (ratio with/without coadministered drug) No Effect = 1
Coadministered Drug | Dose of Coadministered Drug [All doses administered as single dose unless otherwise specified.] | Dose of Metformin HCl |  | AUC [AUC is reported as AUC0-∞ unless otherwise specified.] | Cmax
Glyburide | 5 mg | 500 mg [GLUMETZA (metformin HCl extended-release tablets) 500 mg.] | Metformin | 0.98 [Ratio of arithmetic means.] | 0.99
Furosemide | 40 mg | 850 mg | Metformin | 1.09 | 1.22
Nifedipine | 10 mg | 850 mg | Metformin | 1.16 | 1.21
Propranolol | 40 mg | 850 mg | Metformin | 0.90 | 0.94
Ibuprofen | 400 mg | 850 mg | Metformin | 1.05 | 1.07
Drugs that are eliminated by renal tubular secretion may increase the accumulation of metformin. [see Warnings and Precautions (5.1) and Drug Interactions (7)].
Cimetidine | 400 mg | 850 mg | Metformin | 1.40 | 1.61
Carbonic anhydrase inhibitors may cause metabolic acidosis [see Warnings and Precautions (5.1) and Drug Interactions (7)].
Topiramate | 100 mg [Steady state 100 mg Topiramate every 12 hr + metformin HCl 500 mg every 12 hr AUC = AUC0-12hr.] | 500 mg | Metformin | 1.25 | 1.17

13 NONCLINICAL TOXICOLOGY

13.1 Carcinogenesis, Mutagenesis, Impairment of Fertility

ZITUVIMET

No animal studies have been conducted with the combined products in ZITUVIMET to evaluate carcinogenesis, mutagenesis or impairment of fertility. The following data are based on the findings in studies with sitagliptin and metformin individually.

Sitagliptin

A two-year carcinogenicity study was conducted in male and female rats given oral doses of sitagliptin of 50, 150, and 500 mg/kg/day. There was an increased incidence of combined liver adenoma/carcinoma in males and females and of liver carcinoma in females at 500 mg/kg. This dose results in exposures approximately 60 times the human exposure at the maximum recommended daily adult human dose (MRHD) of 100 mg/day based on AUC comparisons. Liver tumors were not observed at 150 mg/kg, approximately 20 times the human exposure at the MRHD. A two-year carcinogenicity study was conducted in male and female mice given oral doses of sitagliptin of 50, 125, 250, and 500 mg/kg/day. There was no increase in the incidence of tumors in any organ up to 500 mg/kg, approximately 70 times human exposure at the MRHD. Sitagliptin was not mutagenic or clastogenic with or without metabolic activation in the Ames bacterial mutagenicity assay, a Chinese hamster ovary (CHO) chromosome aberration assay, an in vitro cytogenetics assay in CHO, an in vitro rat hepatocyte DNA alkaline elution assay, and an in vivo micronucleus assay.

In rat fertility studies with oral gavage doses of 125, 250, and 1,000 mg/kg, males were treated for 4 weeks prior to mating, during mating, up to scheduled termination (approximately 8 weeks total), and females were treated 2 weeks prior to mating through gestation day 7. No adverse effect on fertility was observed at 125 mg/kg (approximately 12 times human exposure at the MRHD of 100 mg/day based on AUC comparisons). At higher doses, nondose-related increased resorptions in females were observed (approximately 25 and 100 times human exposure at the MRHD based on AUC comparison).

Metformin

Long-term carcinogenicity studies have been performed in rats (dosing duration of 104 weeks) and mice (dosing duration of 91 weeks) at doses up to and including 900 mg/kg/day and 1,500 mg/kg/day, respectively. These doses are both approximately four times the maximum recommended human daily dose of 2,000 mg based on body surface area comparisons. No evidence of carcinogenicity with metformin was found in either male or female mice. Similarly, there was no tumorigenic potential observed with metformin in male rats. There was, however, an increased incidence of benign stromal uterine polyps in female rats treated with 900 mg/kg/day.

There was no evidence of a mutagenic potential of metformin in the following in vitro tests: Ames test (S. typhimurium), gene mutation test (mouse lymphoma cells), or chromosomal aberrations test (human lymphocytes). Results in the in vivo mouse micronucleus test were also negative. Fertility of male or female rats was unaffected by metformin when administered at doses as high as 600 mg/kg/day, which is approximately three times the maximum recommended human daily dose based on body surface area comparisons.

14 CLINICAL STUDIES

The coadministration of sitagliptin and metformin has been evaluated in patients with type 2 diabetes mellitus inadequately controlled on diet and exercise and in combination with other antihyperglycemic agents.

Sitagliptin and Metformin Coadministration in Patients with Type 2 Diabetes Mellitus Inadequately Controlled on Diet and Exercise

A total of 1,091 patients with type 2 diabetes mellitus and inadequate glycemic control on diet and exercise participated in a 24-week, randomized, double-blind, placebo-controlled factorial trial designed to assess the efficacy of sitagliptin and metformin coadministration. Patients on an antihyperglycemic agent (N=541) underwent a diet, exercise, and drug washout period of up to 12 weeks duration. After the washout period, patients with inadequate glycemic control (A1C 7.5% to 11%) were randomized after completing a 2-week single-blind placebo run-in period. Patients not on anti-hyperglycemic agents at trial entry (N=550) with inadequate glycemic control (A1C 7.5% to 11%) immediately entered the 2-week single-blind placebo run-in period and then were randomized. Approximately equal numbers of patients were randomized to receive placebo, 100 mg of sitagliptin once daily, 500 mg or 1,000 mg of metformin HCl twice daily, or 50 mg of sitagliptin twice daily in combination with 500 mg or 1,000 mg of metformin HCl twice daily. Patients who failed to meet specific glycemic goals during the trial were treated with glyburide (glibenclamide) rescue.

Sitagliptin and metformin coadministration provided significant improvements in A1C, FPG, and 2-hour PPG compared to placebo, to metformin alone, and to sitagliptin alone (Table 9, Figure 1). Mean reductions from baseline in A1C were generally greater for patients with higher baseline A1C values. For patients not on an antihyperglycemic agent at trial entry, mean reductions from baseline in A1C were: sitagliptin 100 mg once daily, -1.1%; metformin HCl 500 mg bid, -1.1%; metformin HCl 1,000 mg bid, -1.2%; sitagliptin 50 mg bid with metformin HCl 500 mg bid, -1.6%; sitagliptin 50 mg bid with metformin HCl 1,000 mg bid, -1.9%; and for patients receiving placebo, -0.2%. Lipid effects were generally neutral. The decrease in body weight in the groups given sitagliptin in combination with metformin was similar to that in the groups given metformin alone or placebo.

Table 9: Glycemic Parameters at Final Visit (24-Week Trial) for Sitagliptin and Metformin, Alone and in Combination in Patients with Type 2 Diabetes Mellitus Inadequately Controlled on Diet and Exercise [Intent-to-treat population using last observation in the trial prior to glyburide (glibenclamide) rescue therapy.]
 | Placebo | Sitagliptin 100 mg once daily | Metformin HCl 500 mg twice daily | Metformin HCl 1,000 mg twice daily | Sitagliptin 50 mg twice daily + Metformin HCl 500 mg twice daily | Sitagliptin 50 mg twice daily + Metformin HCl 1,000 mg twice daily
A1C (%) | N = 165 | N = 175 | N = 178 | N = 177 | N = 183 | N = 178
Baseline (mean) | 8.7 | 8.9 | 8.9 | 8.7 | 8.8 | 8.8
Change from baseline (adjusted mean [Least squares means adjusted for prior antihyperglycemic therapy status and baseline value.]) | 0.2 | -0.7 | -0.8 | -1.1 | -1.4 | -1.9
Difference from placebo (adjusted mean) |  | -0.8 [p<0.001 compared to placebo.] | -1 | -1.3 | -1.6 | -2.1
(95% CI) |  | (-1.1, -0.6) | (-1.2, -0.8) | (-1.5, -1.1) | (-1.8, -1.3) | (-2.3, -1.8)
Patients (%) achieving A1C <7% | 15 (9%) | 35 (20%) | 41 (23%) | 68 (38%) | 79 (43%) | 118 (66%)
% Patients receiving rescue medication | 32 | 21 | 17 | 12 | 8 | 2
FPG (mg/dL) | N = 169 | N = 178 | N = 179 | N = 179 | N = 183 | N = 180
Baseline (mean) | 196 | 201 | 205 | 197 | 204 | 197
Change from baseline (adjusted mean) | 6 | -17 | -27 | -29 | -47 | -64
Difference from placebo (adjusted mean) |  | -23 | -33 | -35 | -53 | -70
(95% CI) |  | (-33, -14) | (-43, -24) | (-45, -26) | (-62, -43) | (-79, -60)
2-hour PPG (mg/dL) | N = 129 | N = 136 | N = 141 | N = 138 | N = 147 | N = 152
Baseline (mean) | 277 | 285 | 293 | 283 | 292 | 287
Change from baseline (adjusted mean) | 0 | -52 | -53 | -78 | -93 | -117
Difference from placebo (adjusted mean) |  | -52 | -54 | -78 | -93 | -117
(95% CI) |  | (-67, -37) | (-69, -39) | (-93, -63) | (-107, -78) | (-131, -102)

Figure 1: Mean Change from Baseline for A1C (%) over 24 Weeks with Sitagliptin and Metformin, Alone and in Combination in Patients with Type 2 Diabetes Mellitus Inadequately Controlled with Diet and Exercise*

*All Patients Treated Population: least squares means adjusted for prior antihyperglycemic therapy and baseline value.

Initial combination therapy or maintenance of combination therapy should be individualized and are left to the discretion of the health care provider.

Sitagliptin Add-on Therapy in Patients with Type 2 Diabetes Mellitus Inadequately Controlled on Metformin Alone

A total of 701 patients with type 2 diabetes mellitus participated in a 24-week, randomized, double-blind, placebo-controlled trial designed to assess the efficacy of sitagliptin in combination with metformin. Patients already on metformin (N=431) at a dose of at least 1,500 mg per day were randomized after completing a 2-week, single-blind placebo run-in period. Patients on metformin and another antihyperglycemic agent (N=229) and patients not on any antihyperglycemic agents (off therapy for at least 8 weeks, N=41) were randomized after a run-in period of approximately 10 weeks on metformin HCl (at a dose of at least 1,500 mg per day) in monotherapy. Patients were randomized to the addition of either 100 mg of sitagliptin or placebo, administered once daily. Patients who failed to meet specific glycemic goals during the studies were treated with pioglitazone rescue.

In combination with metformin, sitagliptin provided significant improvements in A1C, FPG, and 2-hour PPG compared to placebo with metformin (Table 10). Rescue glycemic therapy was used in 5% of patients treated with sitagliptin 100 mg and 14% of patients treated with placebo. A similar decrease in body weight was observed for both treatment groups.

Table 10: Glycemic Parameters at Final Visit (24-Week Trial) of Sitagliptin as Add-on Combination Therapy with Metformin [Intent-to-treat population using last observation on trial prior to pioglitazone rescue therapy.]
 | Sitagliptin 100 mg once daily + Metformin | Placebo + Metformin
A1C (%) | N = 453 | N = 224
Baseline (mean) | 8 | 8
Change from baseline (adjusted mean [Least squares means adjusted for prior antihyperglycemic therapy and baseline value.]) | -0.7 | -0
Difference from placebo + metformin (adjusted mean) (95% CI) | -0.7 [p<0.001 compared to placebo + metformin.] (-0.8, -0.5)
Patients (%) achieving A1C <7% | 213 (47%) | 41 (18%)
FPG (mg/dL) | N = 454 | N = 226
Baseline (mean) | 170 | 174
Change from baseline (adjusted mean) | -17 | 9
Difference from placebo + metformin (adjusted mean) (95% CI) | -25 (-31, -20)
2-hour PPG (mg/dL) | N = 387 | N = 182
Baseline (mean) | 275 | 272
Change from baseline (adjusted mean) | -62 | -11
Difference from placebo + metformin (adjusted mean) (95% CI) | -51 (-61, -41)

Sitagliptin Add-on Therapy in Patients with Type 2 Diabetes Mellitus Inadequately Controlled on the Combination of Metformin and Glimepiride

A total of 441 patients with type 2 diabetes mellitus participated in a 24-week, randomized, double-blind, placebo-controlled trial designed to assess the efficacy of sitagliptin in combination with glimepiride, with or without metformin. Patients entered a run-in treatment period on glimepiride (≥4 mg per day) alone or glimepiride in combination with metformin HCl (≥1,500 mg per day). After a dose-titration and dose-stable run-in period of up to 16 weeks and a 2-week placebo run-in period, patients with inadequate glycemic control (A1C 7.5% to 10.5%) were randomized to the addition of either 100 mg of sitagliptin or placebo, administered once daily. Patients who failed to meet specific glycemic goals during the studies were treated with pioglitazone rescue.

Patients receiving sitagliptin with metformin and glimepiride had significant improvements in A1C and FPG compared to patients receiving placebo with metformin and glimepiride (Table 11), with mean reductions from baseline relative to placebo in A1C of -0.9% and in FPG of -21 mg/dL. Rescue therapy was used in 8% of patients treated with add-on sitagliptin 100 mg and 29% of patients treated with add-on placebo. The patients treated with add-on sitagliptin had a mean increase in body weight of 1.1 kg vs. add-on placebo (+0.4 kg vs. -0.7 kg). In addition, add-on sitagliptin resulted in an increased rate of hypoglycemia compared to add-on placebo. [see Warnings and Precautions (5.6) and Adverse Reactions (6.1)].

Table 11: Glycemic Parameters at Final Visit (24-Week Trial) for Sitagliptin in Combination with Metformin and Glimepiride [Intent-to-treat population using last observation on trial prior to pioglitazone rescue therapy.]
 | Sitagliptin 100 mg + Metformin and Glimepiride | Placebo + Metformin and Glimepiride
A1C (%) | N = 115 | N = 105
Baseline (mean) | 8.3 | 8.3
Change from baseline (adjusted mean [Least squares means adjusted for prior antihyperglycemic therapy status and baseline value.]) | -0.6 | 0.3
Difference from placebo (adjusted mean) (95% CI) | -0.9 [p<0.001 compared to placebo.] (-1.1, -0.7)
Patients (%) achieving A1C <7% | 26 (23%) | 1 (1%)
FPG (mg/dL) | N = 115 | N = 109
Baseline (mean) | 179 | 179
Change from baseline (adjusted mean) | -8 | 13
Difference from placebo (adjusted mean) (95% CI) | -21 (-32, -10)

Sitagliptin Add-on Therapy in Patients with Type 2 Diabetes Mellitus Inadequately Controlled on the Combination of Metformin and Rosiglitazone

A total of 278 patients with type 2 diabetes mellitus participated in a 54-week, randomized, double-blind, placebo-controlled trial designed to assess the efficacy of sitagliptin in combination with metformin and rosiglitazone. Patients on dual therapy with metformin HCl ≥1,500 mg/day and rosiglitazone ≥4 mg/day or with metformin HCl ≥1,500 mg/day and pioglitazone ≥30 mg/day (switched to rosiglitazone ≥4 mg/day) entered a dose-stable run-in period of 6 weeks. Patients on other dual therapy were switched to metformin HCl ≥1,500 mg/day and rosiglitazone ≥4 mg/day in a dose titration/stabilization run-in period of up to 20 weeks in duration. After the run-in period, patients with inadequate glycemic control (A1C 7.5% to 11%) were randomized 2:1 to the addition of either 100 mg of sitagliptin or placebo, administered once daily. Patients who failed to meet specific glycemic goals during the trials were treated with glipizide (or other sulfonylurea) rescue. The primary time point for evaluation of glycemic parameters was Week 18.

In combination with metformin and rosiglitazone, sitagliptin provided significant improvements in A1C, FPG, and 2-hour PPG compared to placebo with metformin and rosiglitazone (Table 12) at Week 18. At Week 54, mean reduction in A1C was -1% for patients treated with sitagliptin and -0.3% for patients treated with placebo in an analysis based on the intent-to-treat population. Rescue therapy was used in 18% of patients treated with sitagliptin 100 mg and 40% of patients treated with placebo. There was no significant difference between sitagliptin and placebo in body weight change.

Table 12: Glycemic Parameters at Week 18 for Sitagliptin in Add-on Combination Therapy with Metformin and Rosiglitazone [Intent-to-treat population using last observation in the trial prior to glipizide (or other sulfonylurea) rescue therapy.]
 | Week 18
 | Sitagliptin 100 mg + Metformin + Rosiglitazone | Placebo + Metformin + Rosiglitazone
A1C (%) | N = 176 | N = 93
Baseline (mean) | 8.8 | 8.7
Change from baseline (adjusted mean [Least squares means adjusted for prior antihyperglycemic therapy status and baseline value.]) | -1 | -0.4
Difference from placebo + rosiglitazone + metformin (adjusted mean) (95% CI) | -0.7 [p<0.001 compared to placebo + metformin + rosiglitazone.] (-0.9,-0.4)
Patients (%) achieving A1C <7% | 39 (22%) | 9 (10%)
FPG (mg/dL) | N = 179 | N = 94
Baseline (mean) | 181 | 182
Change from baseline (adjusted mean) | -30 | -11
Difference from placebo + rosiglitazone + metformin (adjusted mean) (95% CI) | -18 (-26, -10)
2-hour PPG (mg/dL) | N = 152 | N = 80
Baseline (mean) | 256 | 248
Change from baseline (adjusted mean) | -59 | -21
Difference from placebo + rosiglitazone + metformin (adjusted mean) (95% CI) | -39 (-51, -26)

Sitagliptin Add-on Therapy in Patients with Type 2 Diabetes Mellitus Inadequately Controlled on the Combination of Metformin and Insulin

A total of 641 patients with type 2 diabetes mellitus participated in a 24-week, randomized, double-blind, placebo-controlled trial designed to assess the efficacy of sitagliptin as add-on to insulin therapy. Approximately 75% of patients were also taking metformin. Patients entered a 2-week, single-blind run-in treatment period on pre-mixed, long-acting, or intermediate-acting insulin, with or without metformin HCl (≥1,500 mg per day). Patients using short-acting insulins were excluded unless the short-acting insulin was administered as part of a pre-mixed insulin. After the run-in period, patients with inadequate glycemic control (A1C 7.5% to 11%) were randomized to the addition of either 100 mg of sitagliptin (N=229) or placebo (N=233), administered once daily. Patients were on a stable dose of insulin prior to enrollment with no changes in insulin dose permitted during the run-in period. Patients who failed to meet specific glycemic goals during the double-blind treatment period were to have uptitration of the background insulin dose as rescue therapy.

Among patients also receiving metformin, the median daily insulin (pre-mixed, intermediate or long acting) dose at baseline was 40 units in the sitagliptin-treated patients and 42 units in the placebo-treated patients. The median change from baseline in daily dose of insulin was zero for both groups at the end of the trial. Patients receiving sitagliptin with metformin and insulin had significant improvements in A1C, FPG and 2-hour PPG compared to patients receiving placebo with metformin and insulin (Table 13). The adjusted mean change from baseline in body weight was -0.3 kg in patients receiving sitagliptin with metformin and insulin and -0.2 kg in patients receiving placebo with metformin and insulin. There was an increased rate of hypoglycemia in patients treated with sitagliptin. [see Warnings and Precautions (5.6) and Adverse Reactions (6.1)].

Table 13: Glycemic Parameters at Final Visit (24-Week Trial) for Sitagliptin as Add-on Combination Therapy with Metformin and Insulin [Intent-to-treat population using last observation on trial prior to rescue therapy.]
 | Sitagliptin 100 mg + Metformin + Insulin | Placebo + Metformin + Insulin
A1C (%) | N = 223 | N = 229
Baseline (mean) | 8.7 | 8.6
Change from baseline (adjusted mean [Least squares means adjusted for insulin use at the screening visit, type of insulin used at the screening visit (pre-mixed vs. non pre-mixed [intermediate- or long-acting]), and baseline value.] , [Treatment by insulin stratum interaction was not significant (p >0.10).]) | -0.7 | -0.1
Difference from placebo (adjusted mean) (95% CI) | -0.5 [p<0.001 compared to placebo.] (-0.7, -0.4)
Patients (%) achieving A1C <7% | 32 (14%) | 12 (5%)
FPG (mg/dL) | N = 225 | N = 229
Baseline (mean) | 173 | 176
Change from baseline (adjusted mean) | -22 | -4
Difference from placebo (adjusted mean) (95% CI) | -18 (-28, -8.4)
2-hour PPG (mg/dL) | N = 182 | N = 189
Baseline (mean) | 281 | 281
Change from baseline (adjusted mean) | -39 | 1
Difference from placebo (adjusted mean) (95% CI) | -40 (-53, -28)

Maintenance of Sitagliptin During Initiation and Titration of Insulin Glargine

A total of 746 patients with type 2 diabetes (mean baseline HbA1C 8.8%, disease duration 10.8 years) participated in a 30-week, randomized, double-blind, placebo-controlled study to assess the efficacy and safety of continuing sitagliptin during the initiation and uptitration of insulin glargine. Patients who were on a stable dose of metformin HCl (≥1,500 mg/day) in combination with a DPP-4 inhibitor and/or sulfonylurea but with inadequate glycemic control (A1C 7.5% to 11%) were enrolled in the study. Those on metformin and sitagliptin (100 mg/day) directly entered the double-blind treatment period; those on another DPP-4 inhibitor and/or on a sulfonylurea entered a 4 to 8 week run-in period in which they were maintained on metformin and switched to sitagliptin (100 mg); other DPP-4 inhibitors and sulfonylureas were discontinued. At randomization patients were randomized either to continue sitagliptin or to discontinue sitagliptin and switch to a matching placebo. On the day of randomization, insulin glargine was initiated at a dose of 10 units subcutaneously in the evening. Patients were instructed to uptitrate their insulin dose in the evening based on fasting blood glucose measurements to achieve a target of 72 to 100 mg/dL.

At 30 weeks, the mean reduction in A1C was greater in the sitagliptin group than in the placebo group (Table 14). At the end of the trial, 27.3% of patients in the sitagliptin group and 27.3% in the placebo group had a fasting plasma glucose (FPG) in the target range; there was no significant difference in insulin dose between arms.

Table 14: Change from Baseline in A1C and FPG at Week 30 in the Maintenance of Sitagliptin During Initiation and Titration of Insulin Glargine Study
 | Sitagliptin 100 mg +Metformin + Insulin Glargine | Placebo +Metformin + Insulin Glargine
A1C (%) | N = 373 [N is the number of randomized and treated patients.] | N = 370
Baseline (mean) | 8.8 | 8.8
Week 30 (mean) | 6.9 | 7.3
Change from baseline (adjusted mean) [Analysis of Covariance including all post-baseline data regardless of rescue or treatment discontinuation. Model estimates calculated using multiple imputation to model washout of the treatment effect using placebo data for all subjects having missing Week 30 data.] | -1.9 | -1.4
Difference from placebo (adjusted mean) (95% CI) | -0.4 (-0.6, -0.3) [p<0.001 compared to placebo.]
Patients (%) with A1C <7% | 202 (54.2%) | 131 (35.4%)
FPG (mg/dL) | N = 373 | N = 370
Baseline (mean) | 199 | 201
Week 30 (mean) | 118 | 123
Change from baseline (adjusted mean) | -81 | -76

Sitagliptin Add-on Therapy vs. Glipizide Add-on Therapy in Patients with Type 2 Diabetes Mellitus Inadequately Controlled on Metformin

The efficacy of sitagliptin was evaluated in a 52-week, double-blind, glipizide-controlled noninferiority trial in patients with type 2 diabetes mellitus. Patients not on treatment or on other antihyperglycemic agents entered a run-in treatment period of up to 12 weeks duration with metformin monotherapy (dose of ≥1,500 mg per day) which included washout of medications other than metformin, if applicable. After the run-in period, those with inadequate glycemic control (A1C 6.5% to 10%) were randomized 1:1 to the addition of sitagliptin 100 mg once daily or glipizide for 52 weeks. Patients receiving glipizide were given an initial dosage of 5 mg/day and then electively titrated over the next 18 weeks to a maximum dosage of 20 mg/day as needed to optimize glycemic control. Thereafter, the glipizide dose was to be kept constant, except for down-titration to prevent hypoglycemia. The mean dose of glipizide after the titration period was 10 mg.

After 52 weeks, sitagliptin and glipizide had similar mean reductions from baseline in A1C in the intent-to-treat analysis (Table 15). These results were consistent with the per protocol analysis (Figure 2). A conclusion in favor of the non-inferiority of sitagliptin to glipizide may be limited to patients with baseline A1C comparable to those included in the trial (over 70% of patients had baseline A1C less than 8% and over 90% had A1C less than 9%).

Table 15: Glycemic Parameters in a 52-Week Trial Comparing Sitagliptin to Glipizide as Add-On Therapy in Patients Inadequately Controlled on Metformin (Intent-to-Treat Population) [The intent-to-treat analysis used the patients' last observation in the trial prior to discontinuation.]
 | Sitagliptin 100 mg + Metformin | Glipizide + Metformin
A1C (%) | N = 576 | N = 559
Baseline (mean) | 7.7 | 7.6
Change from baseline (adjusted mean [Least squares means adjusted for prior antihyperglycemic therapy status and baseline A1C value.]) | -0.5 | -0.6
FPG (mg/dL) | N = 583 | N = 568
Baseline (mean) | 166 | 164
Change from baseline (adjusted mean) | -8 | -8

Figure 2: Mean Change from Baseline for A1C (%) Over 52 Weeks in a Trial Comparing Sitagliptin to Glipizide as Add-On Therapy in Patients Inadequately Controlled on Metformin (Per Protocol Population)*

*The per protocol population (mean baseline A1C of 7.5%) included patients without major protocol violations who had observations at baseline and at Week 52.

The incidence of hypoglycemia in the sitagliptin group (4.9%) was significantly (p<0.001) lower than that in the glipizide group (32%). Patients treated with sitagliptin exhibited a significant mean decrease from baseline in body weight compared to a significant weight gain in patients administered glipizide (-1.5 kg vs. +1.1 kg).

16 HOW SUPPLIED/STORAGE AND HANDLING

Tablets supplied as follows:

Contents | Description | How Supplied | NDC
50 mg sitagliptin and 500 mg metformin HCl | White to off-white, oval shaped, biconvex, film coated tablets debossed with "1786" on one side and plain on the other side. | Bottles of 60 tablets with child-resistant closure. | NDC 70710-1786-6
50 mg sitagliptin and 500 mg metformin HCl | White to off-white, oval shaped, biconvex, film coated tablets debossed with "1786" on one side and plain on the other side. | Bottles of 180 tablets with child-resistant closure. | NDC 70710-1786-8
50 mg sitagliptin and 1,000 mg metformin HCl | Reddish brown, oval shaped, biconvex, film coated tablets debossed with "1787" on one side and plain on the other side | Bottles of 60 tablets with child-resistant closure. | NDC 70710-1787-6
50 mg sitagliptin and 1,000 mg metformin HCl | Reddish brown, oval shaped, biconvex, film coated tablets debossed with "1787" on one side and plain on the other side | Bottles of 180 tablets with child-resistant closure. | NDC 70710-1787-8

Store at 20°C to 25°C (68°F to 77°F), excursions permitted between 15°C and 30°C (59°F and 86°F), [see USP Controlled Room Temperature].

Protect from moisture.

17 PATIENT COUNSELING INFORMATION

Advise the patient to read the FDA-approved patient labeling (Medication Guide).

Lactic Acidosis

Explain the risks of lactic acidosis, its symptoms, and conditions that predispose to its development. Advise patients to discontinue ZITUVIMET immediately and to promptly notify their healthcare provider if unexplained hyperventilation, myalgias, malaise, unusual somnolence or other nonspecific symptoms occur. Counsel patients against excessive alcohol intake and inform patients about the importance of regular testing of renal function while receiving ZITUVIMET. Instruct patients to inform their doctor that they are taking ZITUVIMET prior to any surgical or radiological procedure, as temporary discontinuation may be required [see Warnings and Precautions (5.1)].

Pancreatitis

Inform patients that acute pancreatitis has been reported during postmarketing use of sitagliptin. Inform patients that persistent severe abdominal pain, sometimes radiating to the back, which may or may not be accompanied by vomiting, is the hallmark symptom of acute pancreatitis. Instruct patients to promptly discontinue ZITUVIMET and contact their physician if persistent severe abdominal pain occurs [see Warnings and Precautions (5.2)].

Heart Failure

Inform patients of the signs and symptoms of heart failure. Before initiating ZITUVIMET, ask patients about a history of heart failure or other risk factors for heart failure including moderate to severe renal impairment. Instruct patients to contact their health care provider as soon as possible if they experience symptoms of heart failure, including increasing shortness of breath, rapid increase in weight or swelling of the feet [see Warnings and Precautions (5.3)].

Vitamin B12 Deficiency

Inform patients about the importance of regular monitoring of hematological parameters while receiving ZITUVIMET [see Warnings and Precautions (5.5)].

Hypoglycemia

Inform patients that the incidence of hypoglycemia is increased when ZITUVIMET is added to an insulin secretagogue (e.g., sulfonylurea) or insulin therapy. Explain to patients receiving ZITUVIMET in combination with these medications the risks of hypoglycemia, its symptoms and treatment, and conditions that predispose to its development [see Warnings and Precautions (5.6)].

Hypersensitivity Reactions

Inform patients that allergic reactions have been reported during postmarketing use of sitagliptin, one of the components of ZITUVIMET. If symptoms of allergic reactions (including rash, hives, and swelling of the face, lips, tongue, and throat that may cause difficulty in breathing or swallowing) occur, patients must stop taking ZITUVIMET and seek medical advice promptly.

Severe and Disabling Arthralgia

Inform patients that severe and disabling joint pain may occur with this class of drugs. The time to onset of symptoms can range from one day to years. Instruct patients to seek medical advice if severe joint pain occurs [see Warnings and Precautions (5.8)].

Bullous Pemphigoid

Inform patients that bullous pemphigoid may occur with this class of drugs. Instruct patients to seek medical advice if blisters or erosions occur [see Warnings and Precautions (5.9)].

Females of Reproductive Age:

Inform females that treatment with ZITUVIMET may result in ovulation in some premenopausal anovulatory women which may lead to unintended pregnancy [see Use in Specific Populations (8.3)].

Administration Instructions

Inform patients that the tablets must never be split or divided before swallowing.

The trademarks depicted herein are owned by their respective companies.

Medication Guide available at www.zydususa.com/medguides/ or call 1-877-993-8779

Manufactured by:

Zydus Lifesciences Ltd.,

Pharmez, Matoda, Ahmedabad, India.

Distributed by:

Zydus Pharmaceuticals (USA) Inc.

Route 31 North, Pennington, NJ 08534

Medication Guide
ZITUVIMET® (zye too' vi met)
(sitagliptin and metformin hydrochloride)
tablets, for oral use

Read this Medication Guide carefully before you start taking ZITUVIMET and each time you get a refill. There may be new information. This information does not take the place of talking with your healthcare provider about your medical condition or your treatment. If you have any questions about ZITUVIMET, ask your healthcare provider or pharmacist

What is the most important information I should know about ZITUVIMET?
ZITUVIMET can cause serious side effects , including:
1. Lactic Acidosis. Metformin, one of the medicines in ZITUVIMET, can cause a rare but serious condition called lactic acidosis (a buildup of an acid in the blood) that can cause death. Lactic acidosis is a medical emergency and must be treated in the hospital.
Stop taking ZITUVIMET and call your healthcare provider right away if you have any of the following symptoms, which could be signs of lactic acidosis:

- you feel cold in your hands or feet
- you feel dizzy or lightheaded
- you have a slow or irregular heartbeat
- you feel very weak or tired
- you have unusual (not normal) muscle pain
- you have trouble breathing
- you feel sleepy or drowsy
- you have stomach pains, nausea or vomiting

Most people who have had lactic acidosis with metformin have other things that, combined with the metformin, led to the lactic acidosis. Tell your healthcare provider if you have any of the following, because you have a higher chance for getting lactic acidosis with ZITUVIMET if you:

- have severe kidney problems or your kidneys are affected by certain x-ray tests that use injectable dye have liver problems
- drink alcohol very often, or drink a lot of alcohol in short-term "binge" drinking
- get dehydrated (lose a large amount of body fluids). This can happen if you are sick with a fever, vomiting, or diarrhea.
- Dehydration can also happen when you sweat a lot with activity or exercise and do not drink enough fluids.
- have surgery
- have a heart attack, severe infection, or stroke
- are 65 years of age or older

The best way to keep from having a problem with lactic acidosis from metformin is to tell your healthcare provider if you have any of the problems in the list above. Your healthcare provider may decide to stop your ZITUVIMET for a while if you have any of these things. ZITUVIMET can have other serious side effects. See "What are the possible side effects of ZITUVIMET?"
2. Inflammation of the pancreas (pancreatitis) which may be severe and lead to death. Certain medical problems make you more likely to get pancreatitis.
Before you start taking ZITUVIMET, tell your healthcare provider if you have ever had:
pancreatitis
stones in your gallbladder (gallstones)
high blood triglyceride levels
a history of alcoholism
kidney problems
Stop taking ZITUVIMET and call your healthcare provider right away if you have pain in your stomach area (abdomen) that is severe and will not go away. The pain may be felt going from your abdomen through to your back. The pain may happen with or without vomiting. These may be symptoms of pancreatitis.
3. Heart failure. Heart failure means that your heart does not pump blood well enough.
Before you start taking ZITUVIMET, tell your healthcare provider if you have ever had heart failure or have problems with your kidneys. Contact your healthcare provider right away if you have any of the following symptoms:
increasing shortness of breath or trouble breathing, especially when you lie down
swelling or fluid retention, especially in the feet, ankles, or legs
an unusually fast increase in weight
unusual tiredness
These may be symptoms of heart failure.

What is ZITUVIMET?
ZITUVIMET is a prescription medicine that contains 2 prescription diabetes medicines, sitagliptin and metformin that is used along with diet and exercise to lower blood sugar in adults with type 2 diabetes.
ZITUVIMET is not for people with type 1 diabetes.
If you have had pancreatitis (inflammation of the pancreas) in the past, it is not known if you have a higher chance of getting pancreatitis while you take ZITUVIMET
It is not known if ZITUVIMET is safe and effective in children .

Who should not take ZITUVIMET?
Do not take ZITUVIMET if you:
have severe kidney problems.
have diabetic ketoacidosis.
are allergic to any of the ingredients in ZITUVIMET. See the end of this Medication Guide for a complete list of ingredients in ZITUVIMET.
Symptoms of a serious allergic reaction to ZITUVIMET may include rash, raised red patches on your skin (hives) or swelling of the face, lips, tongue, and throat that may cause difficulty in breathing or swallowing.

What should I tell my healthcare provider before taking ZITUVIMET?
Before you take ZITUVIMET, tell your healthcare provider about all of your medical conditions, including if you:
have or have had inflammation of your pancreas (pancreatitis).
have kidney problems.
have liver problems.
have heart failure.
drink alcohol very often or drink a lot of alcohol in short-term "binge" drinking.
are going to get an injection of dye or contrast agents for an x-ray procedure. ZITUVIMET may need to be stopped for a short time. Talk to your healthcare provider about when you should stop ZITUVIMET and when you should start ZITUVIMET again. See " What is the most important information I should know about ZITUVIMET? "
have low levels of vitamin B12 in your blood.
are pregnant or plan to become pregnant. It is not known if ZITUVIMET will harm your unborn baby. If you are pregnant, talk with your healthcare provider about the best way to control your blood sugar while you are pregnant.
are breastfeeding or plan to breastfeed. It is not known if ZITUVIMET will pass into your breast milk. Talk with your healthcare provider about the best way to feed your baby if you are taking ZITUVIMET.
are a woman who has not gone through menopause (premenopausal) who does not have periods regularly or at all. ZITUVIMET can cause the release of an egg from an ovary in a woman (ovulation). This can increase your chance of getting pregnant. Tell your healthcare provider right away if you become pregnant while taking ZITUVIMET.
Tell your healthcare provider about all the medicines you take , including prescription and over-the-counter medicines, vitamins, and herbal supplements. ZITUVIMET may affect the way other medicines work and other medicines may affect how ZITUVIMET works.
Know the medicines you take. Keep a list of your medicines and show it to your healthcare provider and pharmacist when you get a new medicine.

How should I take ZITUVIMET?
Take ZITUVIMET 2 times a day by mouth. Your healthcare provider will tell you exactly how many ZITUVIMET tablets to take and when you should take them.
Take ZITUVIMET with meals to help to lower your chance of having an upset stomach.
Do not break or cut ZITUVIMET tablets before swallowing. If you cannot swallow ZITUVIMET tablets whole, tell your healthcare provider.
Your healthcare provider may tell you to take ZITUVIMET along with certain other diabetes medicines. Low blood sugar (hypoglycemia) can happen more often when ZITUVIMET is taken with certain other diabetes medicines. See "What are the possible side effects of ZITUVIMET?".
When your body is under some types of stress, such as fever, trauma (such as a car accident), infection or surgery, the amount of diabetes medicine that you need may change. Tell your healthcare provider right away if you have any of these problems and follow your healthcare provider's instructions.
Your healthcare provider will do blood tests to check how well your kidneys are working before and during your treatment with ZITUVIMET
If you take too much ZITUVIMET, call your healthcare provider or Poison Help Line at 1-800-222-1222 or go to the nearest hospital emergency room right away.

What are the possible side effects of ZITUVIMET?
ZITUVIMET may cause serious side effects, including:

- see "What is the most important information I should know about ZITUVIMET?".
- kidney problems, sometimes requiring dialysis.
- low vitamin B12 (vitamin B12 deficiency). Using metformin for long periods of time may cause a decrease in the amount of vitamin B12 in your blood, especially if you have had low vitamin B12 blood levels before. Your healthcare provider may do blood tests to check your vitamin B12 levels.
- low blood sugar (hypoglycemia). If you take ZITUVIMET with another medicine that can cause low blood sugar, such as a sulfonylurea or insulin, your risk of getting low blood sugar is higher. The dose of your sulfonylurea medicine or insulin may need to be lowered while you use ZITUVIMET. Signs and symptoms of low blood sugar may include:

o headache

o drowsiness

o irritability

o hunger

o dizziness

o confusion

o sweating

o feeling jittery

o weakness

o fast heart beat

- Serious allergic reactions. If you have any symptoms of a serious allergic reaction, stop taking ZITUVIMET and call your healthcare provider right away or get emergency medical help. See " Who should not take ZITUVIMET?". Your healthcare provider may give you a medicine for your allergic reaction and prescribe a different medicine for your diabetes.
- Joint pain. Some people who take medicines called DPP-4 inhibitors, one of the medicines in ZITUVIMET, may develop joint pain that can be severe. Call your healthcare provider if you have severe joint pain.
- Skin reaction. Some people who take medicines called DPP-4 inhibitors, one of the medicines in ZITUVIMET, may develop a skin reaction called bullous pemphigoid that can require treatment in a hospital. Tell your healthcare provider right away if you develop blisters or the breakdown of the outer layer of your skin (erosion). Your healthcare provider may tell you to stop taking ZITUVIMET.

The most common side effects of ZITUVIMET include:

- stuffy or runny nose and sore throat
- upper respiratory infection
- low blood sugar (hypoglycemia) when used in combination with certain medicines, such as a sulfonylurea or insulin
- gas, upset stomach, indigestion
- weakness
- nausea and vomiting
- headache
- diarrhea

Taking ZITUVIMET with meals can help lessen the common stomach side effects of metformin that usually happen at the beginning of treatment. If you have unusual or sudden stomach problems, talk with your healthcare provider. Stomach problems that start later during treatment may be a sign of something more serious.
ZITUVIMET may have other side effects, including swelling of the hands or legs . Swelling of the hands and legs can happen if you take ZITUVIMET in combination with rosiglitazone (Avandia). Rosiglitazone is another type of diabetes medicine.
Tell your healthcare provider if you have any side effect that bothers you, or does not go away.
These are not all the possible side effects of ZITUVIMET. For more information, ask your healthcare provider or pharmacist.
Call your healthcare provider for medical advice about side effects. You may report side effects to FDA at 1-800-FDA-1088.

How should I store ZITUVIMET?

- Store ZITUVIMET at room temperature, between 68°F to 77°F (20°C to 25°C).
- Protect it from moisture.

Keep ZITUVIMET and all medicines out of the reach of children.

General information about the safe and effective use of ZITUVIMET.
Medicines are sometimes prescribed for purposes other than those listed in a Medication Guide. Do not use ZITUVIMET for a condition for which it was not prescribed. Do not give ZITUVIMET to other people, even if they have the same symptoms you have. It may harm them.
. You can ask your healthcare provider or pharmacist for information about ZITUVIMET that is written for health professionals.

What are the ingredients in ZITUVIMET?
Active ingredients: sitagliptin and metformin hydrochloride
Inactive ingredients: colloidal silicon dioxide, croscarmellose sodium, low substituted hydroxypropylcellulose, magnesium stearate, malic acid, microcrystalline cellulose, povidone, and sodium stearyl fumarate.
In addition, the film coating contains the following inactive ingredients: polyethylene glycol, polyvinyl alcohol, talc, and titanium dioxide. The film coating of 50 mg/1,000 mg also contains: FD&C yellow #6 aluminum lake, iron oxide red, and iron oxide yellow.

Manufactured by: Zydus Lifesciences Ltd., Pharmez, Matoda, Ahmedabad, India
Distributed by: Zydus Pharmaceuticals (USA) Inc., Route 31 North, Pennington, NJ 08534
The trademarks depicted herein are owned by their respective companies.
For more information, call 1-877-993-8779, email medicalaffairs@zydusua.com, or go to www.zyususa.com/medguides/

This Medication Guide has been approved by the U.S. Food and Drug Administration.

Revised: 06/2025

PACKAGE LABEL.PRINCIPAL DISPLAY PANEL

NDC 70710-1786-6 in bottle of 60 tablets with child-resistant closure.

Zituvimet®

(sitagliptin and metformin HCl) tablets, 50 mg/500 mg

Dispense the enclosed Medication Guide to each patient.

Rx only

Zydus

NDC 70710-1787-6 in bottle of 60 tablets with child-resistant closure.

Zituvimet®

(sitagliptin and metformin HCl) tablets, 50 mg/1000 mg

Dispense the enclosed Medication Guide to each patient.

Rx only

Zydus